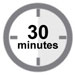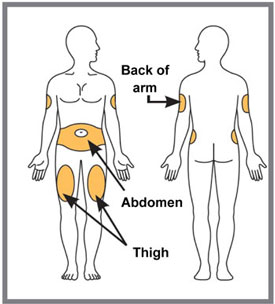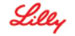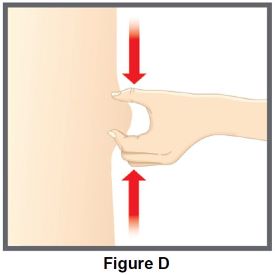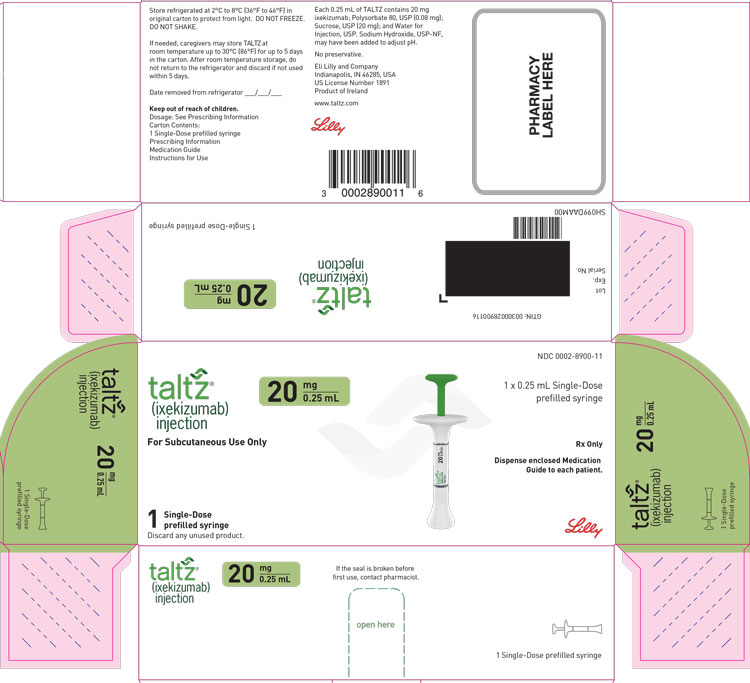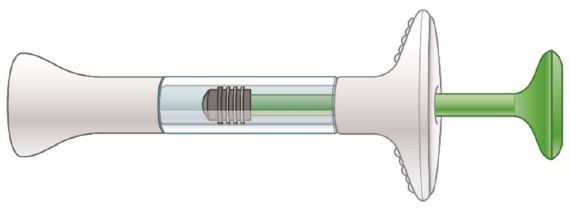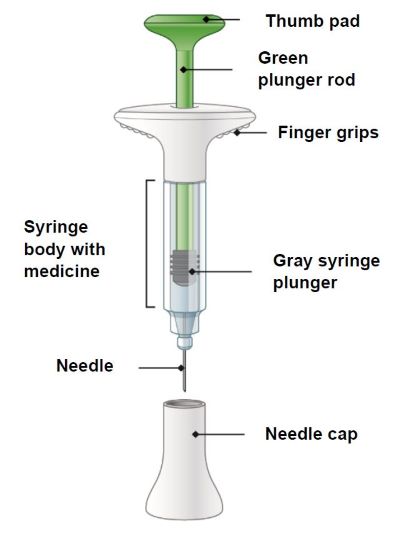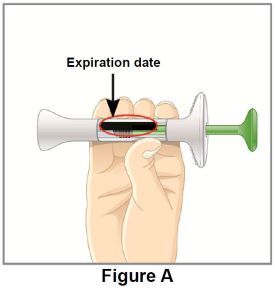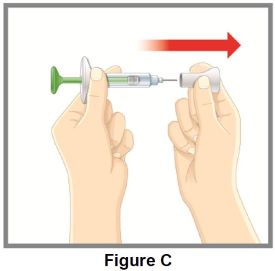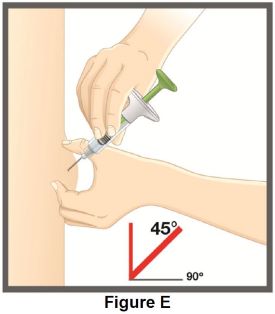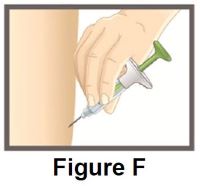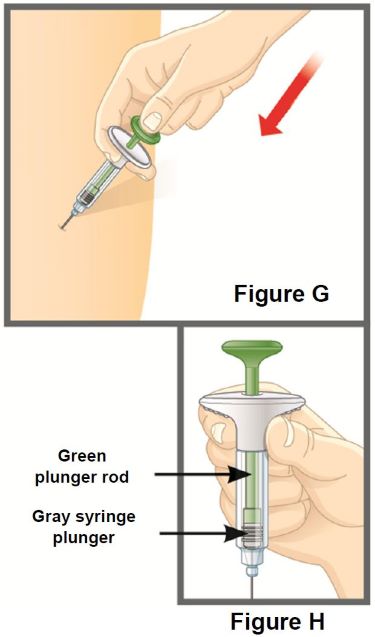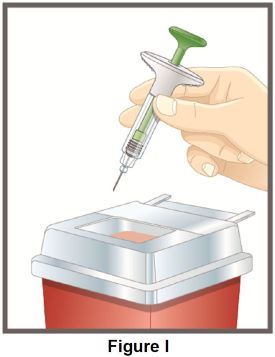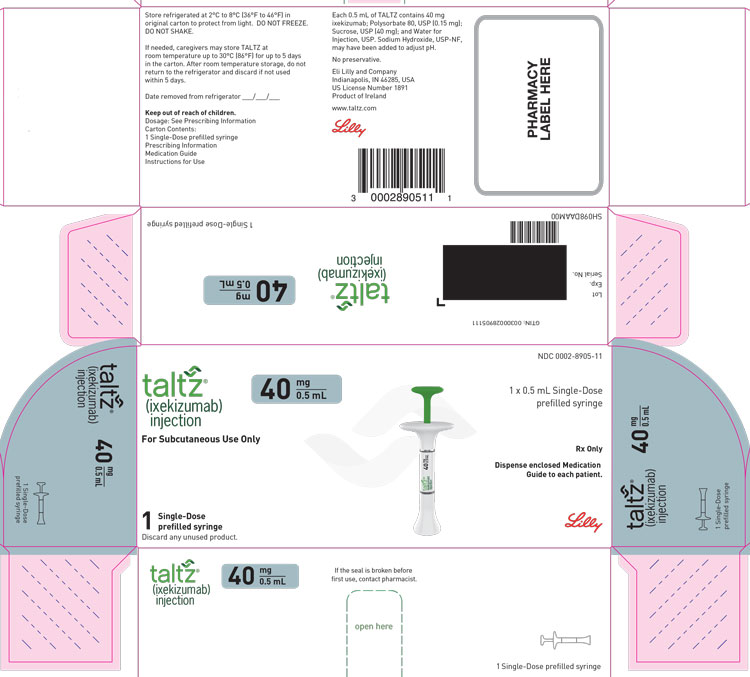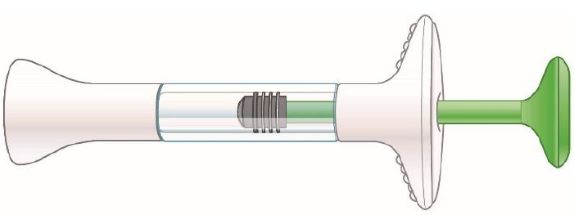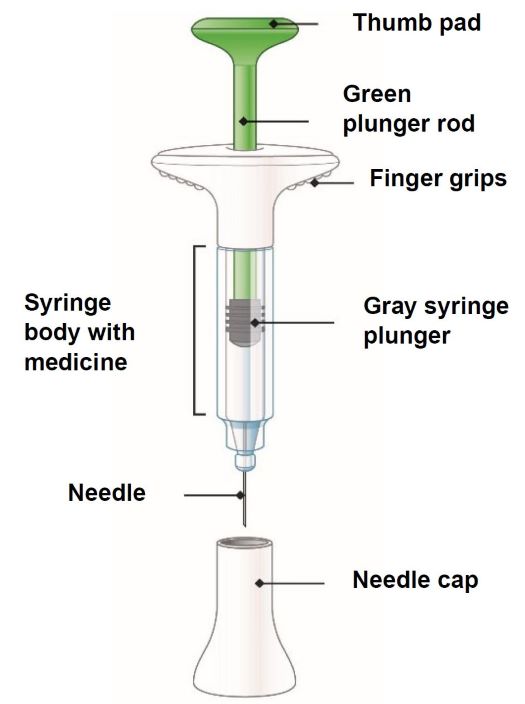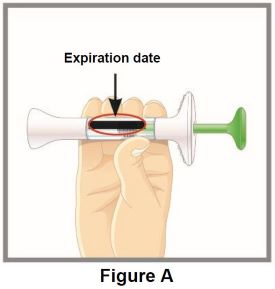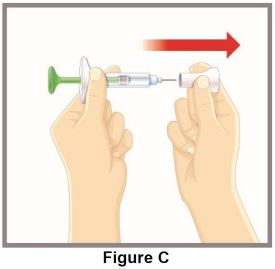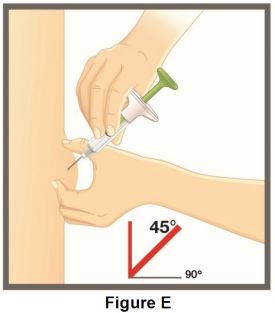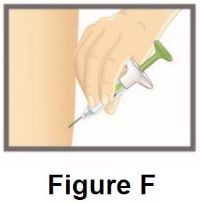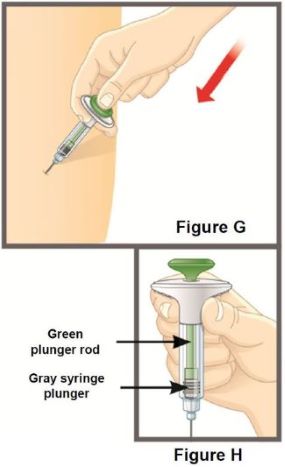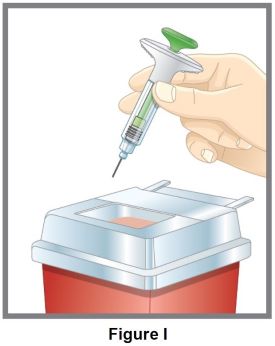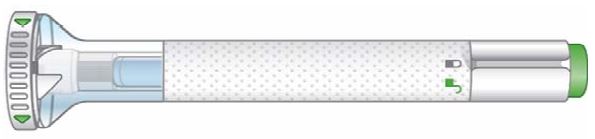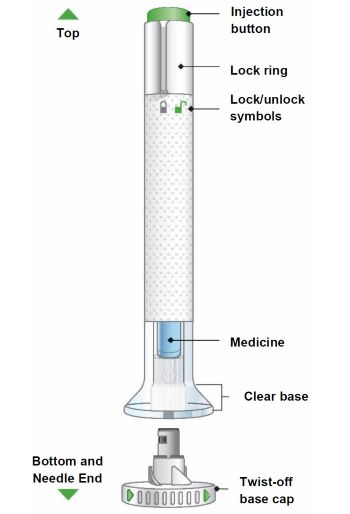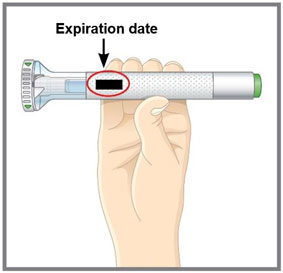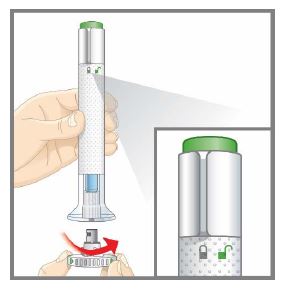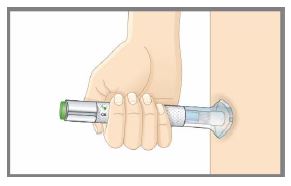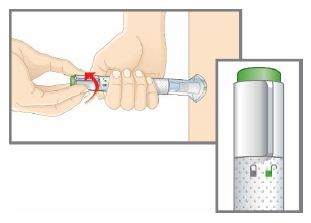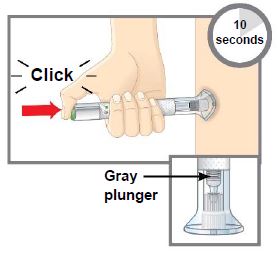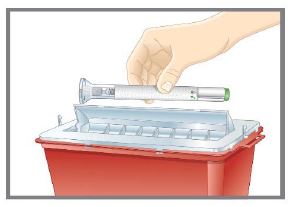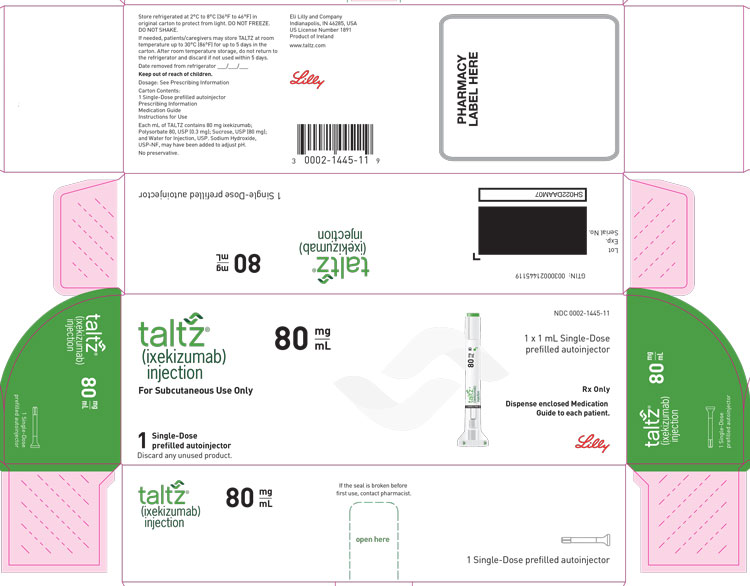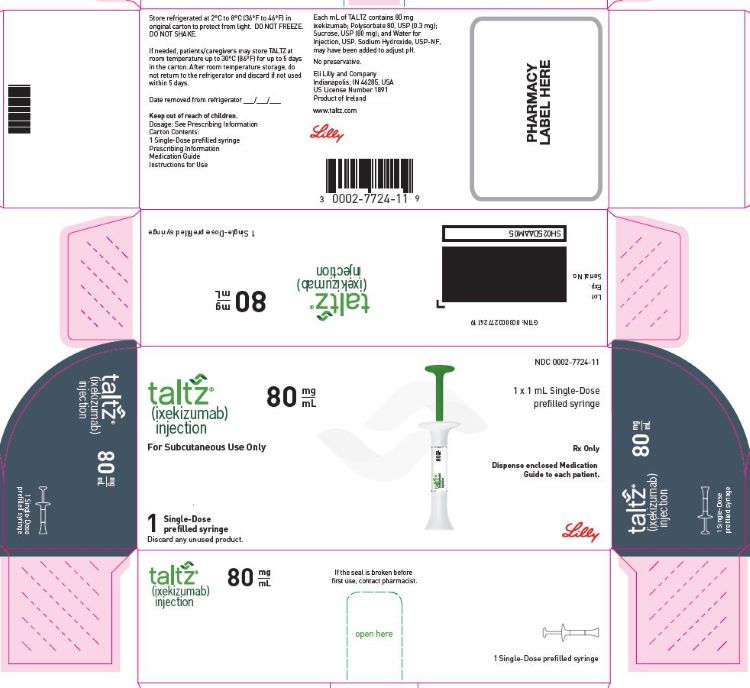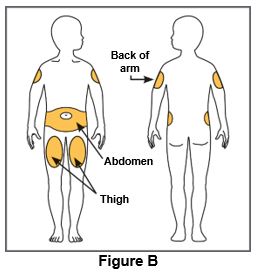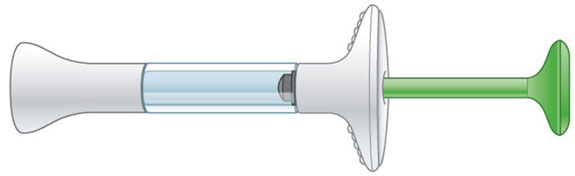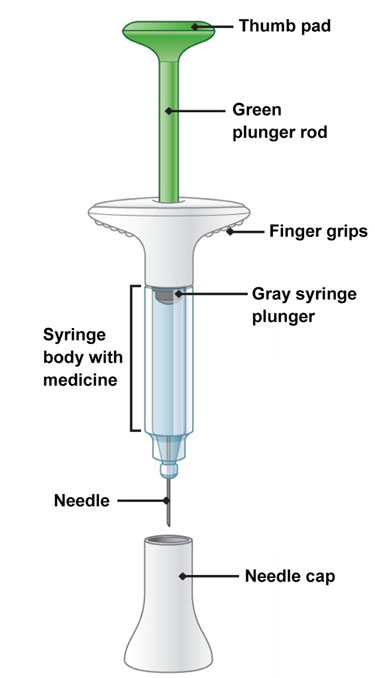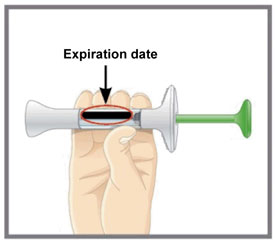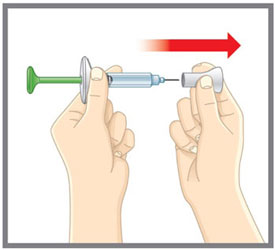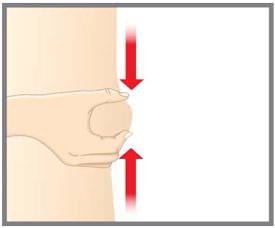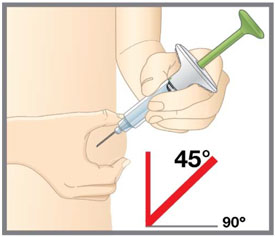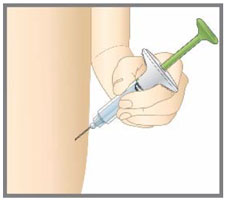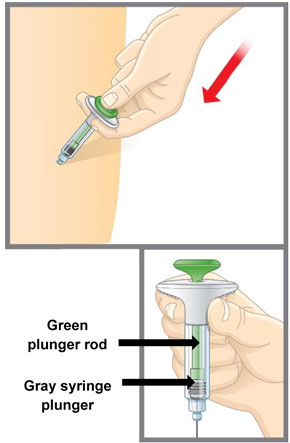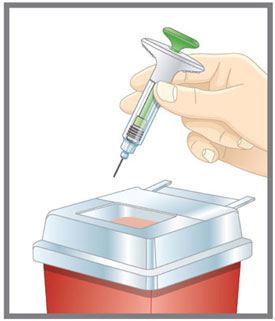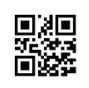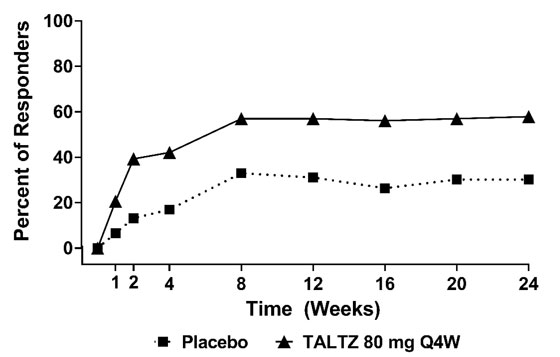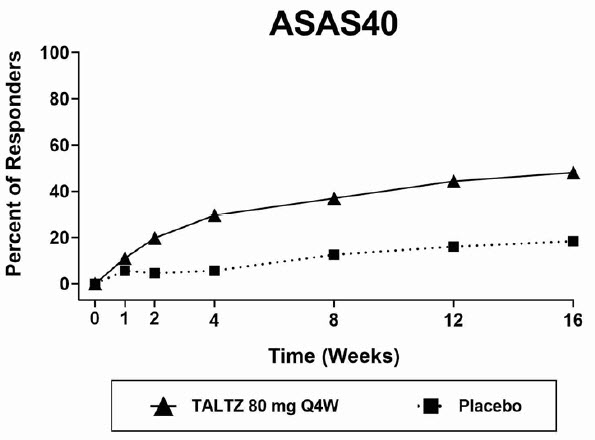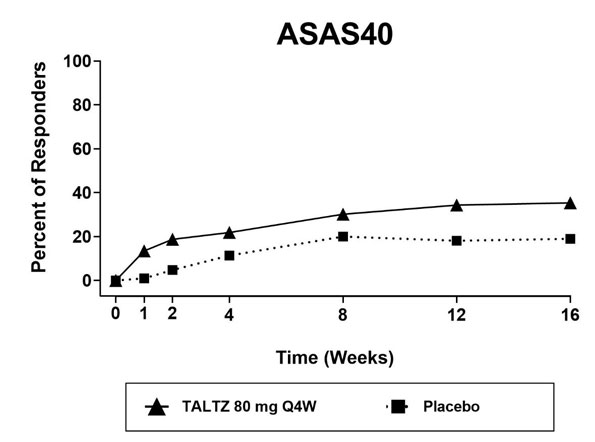 DRUG LABEL: TALTZ
NDC: 0002-1445 | Form: INJECTION, SOLUTION
Manufacturer: Eli Lilly and Company
Category: prescription | Type: HUMAN PRESCRIPTION DRUG LABEL
Date: 20241113

ACTIVE INGREDIENTS: ixekizumab 80 mg/1 mL
INACTIVE INGREDIENTS: Polysorbate 80 0.30 mg/1 mL; Sucrose 80 mg/1 mL; Sodium hydroxide; Water

HIGHLIGHTS OF PRESCRIBING INFORMATION

These highlights do not include all the information needed to use TALTZ safely and effectively. See full prescribing information for TALTZ.
TALTZ (ixekizumab) injection, for subcutaneous use
Initial U.S. Approval: 2016

RECENT MAJOR CHANGES

Dosage and Administration (2.7, 2.8) | 02/2024
Warnings and Precautions (5.1, 5.4) | 08/2024

1 INDICATIONS AND USAGE

TALTZ® is a humanized interleukin-17A antagonist indicated for the treatment of:

- patients aged 6 years or older with moderate-to-severe plaque psoriasis who are candidates for systemic therapy or phototherapy. (1.1)
- adults with active psoriatic arthritis. (1.2)
- adults with active ankylosing spondylitis. (1.3)
- adults with active non-radiographic axial spondyloarthritis with objective signs of inflammation. (1.4)

2 DOSAGE AND ADMINISTRATION

Administer by subcutaneous injection.

Adult Plaque Psoriasis (2.2)

- Recommended dosage is 160 mg (two 80 mg injections) at Week 0, followed by 80 mg at Weeks 2, 4, 6, 8, 10, and 12, then 80 mg every 4 weeks.

Pediatric Plaque Psoriasis (2.3)

- For patients weighing greater than 50 kg, recommended dosage is 160 mg (two 80 mg injections) at Week 0, followed by 80 mg every 4 weeks.
- For patients weighing 25-50 kg, recommended dosage is 80 mg at Week 0, followed by 40 mg every 4 weeks.
- For patients weighing less than 25 kg, recommended dosage is 40 mg at Week 0, followed by 20 mg every 4 weeks.

Psoriatic Arthritis (2.4)

- Recommended dosage is 160 mg by subcutaneous injection (two 80 mg injections) at Week 0, followed by 80 mg every 4 weeks.
- For psoriatic arthritis patients with coexistent moderate-to-severe plaque psoriasis, use the dosing regimen for adult plaque psoriasis. (2.2)
- TALTZ may be administered alone or in combination with a conventional DMARD (e.g., methotrexate).

Ankylosing Spondylitis (2.5)

- Recommended dosage is 160 mg by subcutaneous injection (two 80 mg injections) at Week 0, followed by 80 mg every 4 weeks.

Non-radiographic Axial Spondyloarthritis (2.6)

- Recommended dosage is 80 mg by subcutaneous injection every 4 weeks.

3 DOSAGE FORMS AND STRENGTHS

Injection: (3)

- 80 mg/mL solution in a single-dose prefilled autoinjector
- 80 mg/mL solution in a single-dose prefilled syringe
- 40 mg/0.5 mL solution in a single-dose prefilled syringe
- 20 mg/0.25 mL solution in a single-dose prefilled syringe

4 CONTRAINDICATIONS

Serious hypersensitivity reaction to ixekizumab or to any of the excipients. (4)

5 WARNINGS AND PRECAUTIONS

- Infections: Serious infections have occurred. Instruct patients to seek medical advice if signs or symptoms of clinically important chronic or acute infection occur. If a serious infection develops, discontinue TALTZ until the infection resolves. (5.1)
- Tuberculosis (TB): Evaluate for TB prior to initiating treatment. (5.2)
- Hypersensitivity: If a serious allergic reaction occurs, discontinue TALTZ immediately and initiate appropriate therapy. (5.3)
- Eczematous Eruptions: In the postmarketing setting, cases of severe eczematous eruptions were reported in patients receiving TALTZ. Treatment may need to be discontinued to resolve the eczematous eruption. (5.4)
- Inflammatory Bowel Disease: Crohn's disease and ulcerative colitis, including exacerbations, occurred during clinical trials. Monitor closely when prescribing TALTZ to patients with inflammatory bowel disease (IBD). Discontinue TALTZ and initiate appropriate medical management if IBD develops. (5.5)
- Immunizations: Avoid use of live vaccines. (5.6)

6 ADVERSE REACTIONS

Most common (≥1%) adverse reactions associated with TALTZ treatment are injection site reactions, upper respiratory tract infections, nausea, and tinea infections. (6.1)

To report SUSPECTED ADVERSE REACTIONS, contact Eli Lilly and Company at 1-800-545-5979 (1-800-LillyRx) or FDA at 1-800-FDA-1088 or www.fda.gov/medwatch.

FULL PRESCRIBING INFORMATION

1 INDICATIONS AND USAGE

1.1 Plaque Psoriasis

TALTZ® is indicated for the treatment of patients 6 years of age and older with moderate-to-severe plaque psoriasis who are candidates for systemic therapy or phototherapy.

1.2 Psoriatic Arthritis

TALTZ is indicated for the treatment of adult patients with active psoriatic arthritis.

1.3 Ankylosing Spondylitis

TALTZ is indicated for the treatment of adult patients with active ankylosing spondylitis.

1.4 Non-radiographic Axial Spondyloarthritis

TALTZ is indicated for the treatment of adult patients with active non-radiographic axial spondyloarthritis (nr-axSpA) with objective signs of inflammation.

2 DOSAGE AND ADMINISTRATION

2.1 Testing and Procedures Prior to Treatment Initiation

Perform the following evaluations prior to TALTZ initiation:

- Evaluate patients for tuberculosis (TB) infection. TALTZ initiation is not recommended in patients with active TB infection. Initiate treatment of latent TB prior to initiation of TALTZ [see Warnings and Precautions (5.2)].
- Complete all age-appropriate vaccinations as recommended by current immunization guidelines prior to initiating treatment with TALTZ [see Warnings and Precautions (5.6)].

2.2 Recommended Dosage in Adult Plaque Psoriasis

TALTZ is administered by subcutaneous injection. The recommended dosage in adults with moderate-to-severe plaque psoriasis is 160 mg (two 80 mg injections) at Week 0, followed by 80 mg at Weeks 2, 4, 6, 8, 10, and 12, then 80 mg every 4 weeks.

2.3 Recommended Dosage in Pediatric Plaque Psoriasis

TALTZ is administered by subcutaneous injection every 4 weeks (Q4W). The recommended dosage in pediatric patients from 6 to less than 18 years of age with moderate-to-severe plaque psoriasis is based on the following weight categories.

Table 1: Recommended Dosage for Pediatric Patients 6 Years of Age and Older with Plaque Psoriasis
Pediatric Patient's Weight | Starting Dose (Week 0) | Dose every 4 weeks (Q4W) Thereafter
Greater than 50 kg | 160 mg (two 80 mg injections) | 80 mg
25 to 50 kg | 80 mg | 40 mg
Less than 25 kg | 40 mg | 20 mg

2.4 Recommended Dosage in Psoriatic Arthritis

The recommended dosage is 160 mg by subcutaneous injection (two 80 mg injections) at Week 0, followed by 80 mg every 4 weeks.

For psoriatic arthritis patients with coexistent moderate-to-severe plaque psoriasis, use the dosing regimen for adult plaque psoriasis [see Dosage and Administration (2.2)].

TALTZ may be administered alone or in combination with a conventional disease-modifying antirheumatic drug (cDMARD) (e.g., methotrexate).

2.5 Recommended Dosage in Ankylosing Spondylitis

The recommended dosage is 160 mg by subcutaneous injection (two 80 mg injections) at Week 0, followed by 80 mg every 4 weeks.

2.6 Recommended Dosage in Non-radiographic Axial Spondyloarthritis

The recommended dosage is 80 mg by subcutaneous injection every 4 weeks.

2.7 Preparation and Administration Instructions

TALTZ is intended for use under the guidance and supervision of a healthcare provider. Adult patients may self-inject or caregivers may give injections of TALTZ after training in subcutaneous injection technique using the autoinjector or prefilled syringe. Safety and effectiveness of pediatric self-administration has not been established. Therefore, TALTZ should be administered to pediatric patients by a healthcare provider or by a caregiver who has received training and demonstrated proper subcutaneous injection technique.

TALTZ 20 mg and 40 mg doses prepared from the TALTZ 80 mg/mL prefilled syringe should only be administered by a qualified healthcare professional [see Dosage and Administration (2.8)].

The TALTZ “Instructions for Use” contains more detailed instructions on the preparation and administration of TALTZ [see Instructions for Use].

Before injection, remove TALTZ autoinjector or TALTZ prefilled syringe from the refrigerator and allow TALTZ to reach room temperature (30 minutes) without removing the needle cap. Inspect TALTZ visually for particulate matter and discoloration prior to administration. TALTZ is a clear and colorless to slightly yellow solution. Do not use if the liquid contains visible particles, is discolored or cloudy (other than clear and colorless to slightly yellow).

Administer each injection at a different anatomic location (such as upper arms, thighs or any quadrant of abdomen) than the previous injection, and not into areas where the skin is tender, bruised, erythematous, indurated or affected by psoriasis. Administration of TALTZ in the upper, outer arm may be performed by a caregiver or healthcare provider [see Instructions for Use].

TALTZ does not contain preservatives, therefore discard any unused product.

If a dose is missed, administer the dose as soon as possible. Thereafter, resume dosing at the regular scheduled time.

2.8 Alternative Preparation Instructions of TALTZ Doses for Pediatric Patients with Plaque Psoriasis Weighing 50 kg or Less

If the 20 mg/0.25 mL or 40 mg/0.5 mL prefilled syringe is unavailable, TALTZ doses of 20 mg or 40 mg for pediatric patients with plaque psoriasis [see Dosage and Administration (2.3)] must be manually prepared according to the steps below using only the TALTZ 80 mg/mL prefilled syringe. The preparation and administration of the 20 mg and 40 mg doses should only be performed by a qualified healthcare professional. For additional preparation and administration instructions, [see Dosage and Administration (2.7)].

1. Gather the following necessary supplies for preparation:
  - 0.5 mL or 1 mL disposable syringe
  - Sterile needle for withdrawal
  - 27-gauge sterile needle for administration
  - Sterile, clear glass vial.
2. Expel the entire contents of the prefilled syringe into the sterile vial. DO NOT shake or swirl the vial. Do not add other medications to solutions containing TALTZ.
3. Using the 0.5 mL or 1 mL disposable syringe and sterile needle, withdraw the prescribed dose from the vial (0.25 mL for 20 mg; 0.5 mL for 40 mg).
4. Remove the needle from the syringe and replace it with a 27-gauge needle prior to administering TALTZ.

Storage of Prepared TALTZ

If necessary, TALTZ 20 mg or 40 mg doses prepared from an 80 mg/mL prefilled syringe may be stored at room temperature for up to 4 hours from first puncturing the sterile vial.

3 DOSAGE FORMS AND STRENGTHS

TALTZ is a clear and colorless to slightly yellow solution available as:

- Injection: 80 mg/mL solution of TALTZ in a single-dose prefilled autoinjector
- Injection: 80 mg/mL solution of TALTZ in a single-dose prefilled syringe
- Injection: 40 mg/0.5 mL solution of TALTZ in a single-dose prefilled syringe
- Injection: 20 mg/0.25 mL solution of TALTZ in a single-dose prefilled syringe

4 CONTRAINDICATIONS

TALTZ is contraindicated in patients with a previous serious hypersensitivity reaction, such as anaphylaxis, to ixekizumab or to any of the excipients [see Warnings and Precautions (5.3)].

5 WARNINGS AND PRECAUTIONS

5.1 Infections

TALTZ may increase the risk of infection. In clinical trials in adult patients with plaque psoriasis, the TALTZ group had a higher rate of infections than the placebo group (27% vs. 23%). Upper respiratory tract infections, oral candidiasis, conjunctivitis and tinea infections occurred more frequently in the TALTZ group than in the placebo group. A similar increase in risk of infection was seen in placebo-controlled trials in patients with pediatric psoriasis, psoriatic arthritis, ankylosing spondylitis, and non-radiographic axial spondyloarthritis [see Adverse Reactions (6.1)].

In the postmarketing setting, serious bacterial, viral, and fungal opportunistic infections have been reported in patients receiving IL-17 inhibitors including TALTZ. Instruct patients treated with TALTZ to seek medical advice if signs or symptoms of clinically important chronic or acute infection occur. If a patient develops a serious infection or is not responding to standard therapy, monitor the patient closely and discontinue TALTZ until the infection resolves.

5.2 Pre-treatment Evaluation for Tuberculosis

Evaluate patients for tuberculosis (TB) infection prior to initiating treatment with TALTZ. Do not administer to patients with active TB infection. Initiate treatment of latent TB prior to administering TALTZ. Consider anti-TB therapy prior to initiating TALTZ in patients with a past history of latent or active TB in whom an adequate course of treatment cannot be confirmed. Patients receiving TALTZ should be monitored closely for signs and symptoms of active TB during and after treatment.

5.3 Hypersensitivity

Serious hypersensitivity reactions, including angioedema and urticaria (each ≤0.1%), occurred in the TALTZ group in clinical trials. Anaphylaxis, including cases leading to hospitalization, has been reported in post marketing use with TALTZ [see Adverse Reactions (6.1, 6.3)]. If a serious hypersensitivity reaction occurs, discontinue TALTZ immediately and initiate appropriate therapy.

5.4 Eczematous Eruptions

In the postmarketing setting, cases of severe eczematous eruptions, including atopic dermatitis-like eruptions, dyshidrotic eczema, and erythroderma were reported in patients receiving TALTZ; some cases resulted in hospitalization. The onset of eczematous eruptions was variable, ranging from days to months after the first dose of TALTZ. Treatment may need to be discontinued to resolve the eczematous eruption. Some patients with limited psoriasis treatment options were successfully treated for eczema while continuing TALTZ.

5.5 Inflammatory Bowel Disease

Patients treated with TALTZ may be at increased risk of inflammatory bowel disease. In clinical trials, Crohn's disease and ulcerative colitis, including exacerbations, occurred at a greater frequency in the TALTZ group than the placebo control group [see Adverse Reactions (6.1)]. During TALTZ treatment, monitor for onset or exacerbation of inflammatory bowel disease and if IBD occurs, discontinue TALTZ and initiate appropriate medical management.

5.6 Immunizations

Prior to initiating therapy with TALTZ, consider completion of all age-appropriate immunizations according to current immunization guidelines. Avoid use of live vaccines in patients treated with TALTZ. No data are available on the response to live vaccines.

6 ADVERSE REACTIONS

The following adverse drug reactions are discussed in greater detail in other sections of the label:

- Infections [see Warnings and Precautions (5.1)]
- Hypersensitivity Reactions [see Contraindications (4) and Warnings and Precautions (5.3)]
- Eczematous Eruptions [see Warnings and Precautions (5.4)]
- Inflammatory Bowel Disease [see Warnings and Precautions (5.5)]

6.1 Clinical Trials Experience

Because clinical trials are conducted under widely varying and controlled conditions, adverse reaction rates observed in the clinical trials of a drug cannot be directly compared to rates in the clinical trials of another drug and may not reflect the rates observed in practice.

Adult Plaque Psoriasis

Weeks 0 to 12:

Three placebo-controlled trials in subjects with plaque psoriasis were integrated to evaluate the safety of TALTZ compared to placebo for up to 12 weeks. A total of 1167 subjects (mean age 45 years; 66% men; 94% White) with plaque psoriasis received TALTZ (160 mg at Week 0, 80 mg every 2 weeks [Q2W] for 12 weeks) subcutaneously. In two of the trials, the safety of TALTZ (use up to 12 weeks) was also compared with an active comparator, U.S. approved etanercept [see Clinical Studies (14)].

In the 12-week, placebo-controlled period, adverse events occurred in 58% of the TALTZ Q2W group (2.5 per subject-year of follow-up) compared with 47% of the placebo group (2.1 per subject-year of follow-up). Serious adverse events occurred in 2% of the TALTZ group (0.07 per subject-year of follow-up), and in 2% of the placebo group (0.07 per subject-year of follow-up).

Table 2 summarizes the adverse reactions that occurred at a rate of at least 1% and at a higher rate in the TALTZ group than in the placebo group during the 12-week placebo-controlled period of the pooled clinical trials.

Table 2: Adverse Reactions Occurring in ≥1% of the TALTZ Group and More Frequently than in the Placebo Group in the Plaque Psoriasis Clinical Trials through Week 12
Adverse Reactions | TALTZ 80 mg Q2W (N=1167) n (%) | Etanerceptb (N=287) n (%) | Placebo (N=791) n (%)
Injection site reactions | 196 (17) | 32 (11) | 26 (3)
Upper respiratory tract infectionsa | 163 (14) | 23 (8) | 101 (13)
Nausea | 23 (2) | 1 (<1) | 5 (1)
Tinea infections | 17 (2) | 0 | 1 (<1)
a Upper respiratory tract infections cluster includes nasopharyngitis and rhinovirus infection.
b U.S. approved etanercept.

Adverse reactions that occurred at rates less than 1% in the TALTZ group and more frequently than in the placebo group during the 12-week induction period included rhinitis, oral candidiasis, urticaria, influenza, conjunctivitis, inflammatory bowel disease, and angioedema.

Weeks 13 to 60:

A total of 332 subjects received the recommended maintenance regimen of TALTZ 80 mg dosed every 4 weeks.

During the maintenance period (Weeks 13 to 60), adverse events occurred in 80% of subjects treated with TALTZ (1.0 per subject-year of follow-up) compared to 58% of subjects treated with placebo (1.1 per subject-year of follow-up). Serious adverse events were reported in 4% of subjects treated with TALTZ (0.05 per subject-year of follow-up) and none in the subjects treated with placebo.

Weeks 0 to 60:

Over the entire treatment period (Weeks 0 to 60), adverse events were reported in 67% of subjects treated with TALTZ (1.4 per subject-year of follow-up) compared to 48% of subjects treated with placebo (2.0 per subject-year of follow-up). Serious adverse events were reported in 3% of subjects treated with TALTZ (0.06 per subject-year of follow-up), and in 2% of subjects treated with placebo (0.06 per subject-year of follow-up).

Specific Adverse Drug Reactions

Injection Site Reactions

The most frequent injection site reactions were erythema and pain. Most injection site reactions were mild-to-moderate in severity and did not lead to discontinuation of TALTZ.

Infections

In the 12-week, placebo-controlled period of the clinical trials in plaque psoriasis, infections occurred in 27% of subjects treated with TALTZ (1.2 per subject-year of follow-up) compared to 23% of subjects treated with placebo (1.0 per subject-year of follow-up). Serious infections occurred in 0.4% of subjects treated with TALTZ (0.02 per subject-year of follow-up) and in 0.4% of subjects treated with placebo (0.02 per subject-year of follow-up) [see Warnings and Precautions (5.1)].

During the maintenance treatment period (Weeks 13 to 60), infections occurred in 57% of subjects treated with TALTZ (0.70 per subject-year of follow-up) compared to 32% of subjects treated with placebo (0.61 per subject-year of follow-up). Serious infections occurred in 0.9% of subjects treated with TALTZ (0.01 per subject-year of follow-up) and none in the subjects treated with placebo.

Over the entire treatment period (Weeks 0 to 60), infections were reported in 38% of subjects treated with TALTZ (0.83 per subject-year of follow-up) compared to 23% of subjects treated with placebo (1.0 per subject-year of follow-up). Serious infections occurred in 0.7% of subjects treated with TALTZ (0.02 per subject-year of follow-up), and in 0.4% of subject treated with placebo (0.02 per subject-year of follow-up).

Inflammatory Bowel Disease

In adult subjects with plaque psoriasis, Crohn's disease and ulcerative colitis, including exacerbations, occurred at a greater frequency in the TALTZ 80 mg Q2W group (Crohn's disease 0.1%, ulcerative colitis 0.2%) than the placebo group (0%) during the 12-week, placebo-controlled period in clinical trials [see Warnings and Precautions (5.5)].

Laboratory Assessment of Cytopenia

Neutropenia

Over the entire treatment period (Weeks 0 to 60), neutropenia occurred in 11% of subjects treated with TALTZ (0.24 per subject-year of follow-up) compared to 3% of subjects treated with placebo (0.14 per subject-year of follow-up). In subjects treated with TALTZ, the incidence rate of neutropenia during Weeks 13 to 60 was lower than the incidence rate during Weeks 0 to 12.

In the 12-week, placebo-controlled period, neutropenia ≥ Grade 3 (<1,000 cells/mm^3) occurred in 0.2% of the TALTZ group (0.007 per subject-year of follow-up) compared to 0.1% of the placebo group (0.006 per subject-year of follow-up). The majority of cases of neutropenia were either Grade 2 (2% for TALTZ 80 mg Q2W versus 0.3% for placebo; ≥1,000 to <1,500 cells/mm^3) or Grade 1 (7% for TALTZ 80 mg Q2W versus 3% for placebo; ≥1,500 cells/mm^3 to ˂2,000 cells/mm^3). Neutropenia in the TALTZ group was not associated with an increased rate of infection compared to the placebo group.

Thrombocytopenia

Ninety eight percent of cases of thrombocytopenia were Grade 1 (3% for TALTZ 80 mg Q2W versus 1% for placebo; ≥75,000 cells/mm^3 to <150,000 cells/mm^3). Thrombocytopenia in subjects treated with TALTZ was not associated with an increased rate of bleeding compared to subjects treated with placebo.

Active Comparator Trials

In the two clinical trials that included an active comparator, the rate of serious adverse events during weeks zero to twelve was 0.7% for U.S. approved etanercept and 2% for TALTZ 80 mg Q2W, and the rate of discontinuation from adverse events was 0.7% for U.S. approved etanercept and 2% for TALTZ 80 mg Q2W. The incidence of infections was 18% for U.S. approved etanercept and 26% for TALTZ 80 mg Q2W. The rate of serious infections was 0.3% for both TALTZ 80 mg Q2W and U.S. approved etanercept.

Pediatric Plaque Psoriasis

TALTZ was evaluated in a placebo-controlled trial in pediatric subjects with moderate-to-severe psoriasis 6 to less than 18 years of age. A total of 171 subjects were studied (115 subjects on TALTZ and 56 subjects on placebo). Overall, the safety profile observed in pediatric subjects with plaque psoriasis treated with TALTZ every 4 weeks is consistent with the safety profile in adult subjects with plaque psoriasis with the exception of the frequencies of conjunctivitis (2.6%), influenza (1.7%), and urticaria (1.7%).

In this clinical trial, Crohn's disease occurred at a greater frequency in the TALTZ group (0.9%) than the placebo group (0%) during the 12-week, placebo-controlled period. Crohn's disease occurred in a total of 4 TALTZ treated subjects (2.0%) in the clinical trial [see Warnings and Precautions (5.5)].

Psoriatic Arthritis

TALTZ was studied in two placebo-controlled trials in patients with psoriatic arthritis. A total of 678 patients were studied (454 patients on TALTZ and 224 on placebo). A total of 229 patients in these trials received TALTZ 160 mg at Week 0, followed by 80 mg every 4 weeks (Q4W). Overall, the safety profile observed in patients with psoriatic arthritis treated with TALTZ Q4W is consistent with the safety profile in adult patients with plaque psoriasis with the exception of the frequencies of influenza (1.3%) and conjunctivitis (1.3%).

Ankylosing Spondylitis

TALTZ was studied in two placebo-controlled trials in patients with ankylosing spondylitis. A total of 566 patients were studied (376 patients on TALTZ and 190 on placebo). A total of 195 patients in these trials received TALTZ 80 or 160 mg at Week 0, followed by 80 mg every 4 weeks (Q4W). Overall, the safety profile observed in patients with ankylosing spondylitis treated with TALTZ Q4W is consistent with the safety profile in adult patients with plaque psoriasis.

In adult patients with ankylosing spondylitis, Crohn's disease and ulcerative colitis, including exacerbations, occurred in 2 patients (1.0%) and 1 patient (0.5%), respectively, in the TALTZ 80 mg Q4W group and 1 patient (0.5%) and 0%, respectively, in the placebo group during the 16-week, placebo-controlled period in clinical trials. Of these patients, serious events occurred in 1 patient in the TALTZ 80 mg Q4W group and 1 patient in the placebo group [see Warnings and Precautions (5.5)].

Non-radiographic Axial Spondyloarthritis

TALTZ was studied in a placebo-controlled trial in patients with non-radiographic axial spondyloarthritis. A total of 303 patients were studied (198 patients on TALTZ and 105 on placebo). A total of 96 patients in this trial received TALTZ 80 or 160 mg at Week 0, followed by 80 mg every 4 weeks (Q4W). Overall, the safety profile observed in patients with non-radiographic axial spondyloarthritis treated with TALTZ 80 mg Q4W up to Week 16 is consistent with the previous experience of TALTZ in other indications.

6.2 Immunogenicity

As with all therapeutic proteins there is the potential for immunogenicity with TALTZ. The assay to test for neutralizing antibodies has limitations detecting neutralizing antibodies in the presence of ixekizumab; therefore, the incidence of neutralizing antibodies development could be underestimated.

Plaque Psoriasis Population

By Week 12, approximately 9% of adult subjects treated with TALTZ every 2 weeks developed antibodies to ixekizumab. Approximately 22% of subjects treated with TALTZ at the recommended dosing regimen developed antibodies to ixekizumab during the 60-week treatment period. The clinical effects of antibodies to ixekizumab are dependent on the antibody titer; higher antibody titers were associated with decreasing drug concentration and clinical response.

Of the adult subjects who developed antibodies to ixekizumab during the 60-week treatment period, approximately 10%, which equates to 2% of subjects treated with TALTZ at the recommended dosing regimen, had antibodies that were classified as neutralizing. Neutralizing antibodies were associated with reduced drug concentrations and loss of efficacy.

In pediatric psoriasis subjects treated with ixekizumab at the recommended dosing regimen up to 12 weeks, 21 subjects (18%) developed anti-drug antibodies, 5 subjects (4%) had confirmed neutralizing antibodies associated with low drug concentrations. No conclusive evidence could be obtained on the potential association of neutralizing antibodies and clinical response and/or adverse events due to small number of pediatric subjects in the study.

Psoriatic Arthritis Population

For subjects treated with TALTZ 80 mg every 4 weeks for up to 52 weeks (PsA1), 11% developed anti-drug antibodies, and 8% had confirmed neutralizing antibodies.

Ankylosing Spondylitis Population

For patients treated with TALTZ 80 mg every 4 weeks for up to 16 weeks (AS1, AS2), 5.2% developed anti-drug antibodies, and 1.5% had neutralizing antibodies.

Non-radiographic Axial Spondyloarthritis Population

Of patients treated with TALTZ 80 mg every 4 weeks for up to 52 weeks (nr-axSpA1), 8.9% developed anti-drug antibodies, all of which were low titer. No patient had neutralizing antibodies.

The detection of antibody formation is highly dependent on the sensitivity and specificity of the assay. Additionally, the observed incidence of antibody (including neutralizing antibody) positivity in an assay may be influenced by several factors including assay methodology, sample handling, timing of sample collection, concomitant medications, and underlying disease. For these reasons, comparison of incidence of antibodies to TALTZ across indications or with the incidences of antibodies to other products may be misleading.

6.3 Postmarketing Experience

The following adverse reactions have been identified during post-approval use of TALTZ. Because the reactions are reported voluntarily from a population of uncertain size, it is not always possible to reliably estimate their frequency or establish a causal relationship to TALTZ exposure.

Immune system disorders: anaphylaxis [see Contraindications (4)].

Infections: bacterial, viral, and fungal opportunistic infections, including cryptococcal meningoencephalitis, esophageal and disseminated mucocutaneous candidiasis, pulmonary tuberculosis, toxoplasmosis, varicella zoster virus reactivation, cytomegalovirus colitis, pulmonary aspergillosis.

Skin and subcutaneous tissue disorders: Eczematous eruptions (erythroderma, atopic dermatitis-like eruptions, and dyshidrotic eczema).

8 USE IN SPECIFIC POPULATIONS

8.1 Pregnancy

Pregnancy Exposure Registry

There is a pregnancy exposure registry that monitors pregnancy outcomes in women exposed to TALTZ during pregnancy. Pregnant women exposed to TALTZ are encouraged to enroll in the TALTZ Pregnancy Registry by calling 1-800-284-1695. Contact information for the registry is also available on http://www.pregnancyregistry.lilly.com.

Risk Summary

Available data from the published literature and the pharmacovigilance database with TALTZ use in pregnant women are insufficient to evaluate for a drug-associated risk of major birth defects, miscarriage or other adverse maternal or fetal outcomes.

Human IgG is known to cross the placental barrier; therefore, TALTZ may be transmitted from the mother to the developing fetus. An embryofetal development study conducted in pregnant monkeys during organogenesis at doses up to 19 times the maximum recommended human dose (MRHD) revealed no evidence of harm to the developing fetus. When dosing was continued until parturition, neonatal deaths were observed at 1.9 times the MRHD [see Data]. The clinical significance of these nonclinical findings is unknown.

The background risk of major birth defects and miscarriage for the indicated population is unknown. All pregnancies have a background risk of birth defect, loss, or other adverse outcomes. In the U.S. general population, the estimated background risk of major birth defects and miscarriage in clinically recognized pregnancies is 2 to 4% and 15 to 20%, respectively.

Data

Animal Data

An embryofetal development study was conducted in cynomolgus monkeys administered ixekizumab. No malformations or embryofetal toxicity were observed in fetuses from pregnant monkeys administered ixekizumab weekly by subcutaneous injection during organogenesis to near parturition at doses up to 19 times the MRHD (on a mg/kg basis of 50 mg/kg/week). Ixekizumab crossed the placenta in monkeys.

In a pre- and post-natal development toxicity study, pregnant cynomolgus monkeys were administered weekly subcutaneous doses of ixekizumab up to 19 times the MRHD from the beginning of organogenesis to parturition. Neonatal deaths occurred in the offspring of two monkeys administered ixekizumab at 1.9 times the MRHD (on a mg/kg basis of 5 mg/kg/week) and two monkeys administered ixekizumab at 19 times the MRHD (on a mg/kg basis of 50 mg/kg/week). These neonatal deaths were attributed to early delivery, trauma, or congenital defect. The clinical significance of these findings is unknown. No ixekizumab-related effects on functional or immunological development were observed in the surviving infants from birth through 6 months of age.

8.2 Lactation

Risk Summary

There are no available data on the presence of ixekizumab in human milk, the effects on the breastfed infant, or the effects on milk production. Ixekizumab was detected in the milk of lactating cynomolgus monkeys. When a drug is present in animal milk, it is likely that the drug will be present in human milk. The developmental and health benefits of breastfeeding should be considered along with the mother's clinical need for TALTZ and any potential adverse effects on the breastfed infant from TALTZ or from the underlying maternal condition.

8.4 Pediatric Use

The safety and effectiveness of TALTZ have been established in pediatric subjects aged 6 years to less than 18 years with moderate-to-severe plaque psoriasis. The safety and effectiveness of TALTZ in other pediatric indications and for pediatric subjects less than 6 years of age have not been established.

8.5 Geriatric Use

Of the 4204 adult psoriasis subjects exposed to TALTZ, a total of 301 were 65 years or older, and 36 subjects were 75 years or older. Although no differences in safety or efficacy were observed between older and younger subjects, the number of subjects aged 65 and over is not sufficient to determine whether they respond differently from younger subjects [see Clinical Pharmacology (12.3)].

11 DESCRIPTION

Ixekizumab is a humanized immunoglobulin G subclass 4 (IgG4) monoclonal antibody (mAb) with neutralizing activity against IL-17A. Ixekizumab is produced by recombinant DNA technology in a recombinant mammalian cell line and purified using standard technology for bioprocessing. Ixekizumab is comprised of two identical light chain polypeptides of 219 amino acids each and two identical heavy chain polypeptides of 445 amino acids each and has a molecular weight of 146,158 Daltons for the protein backbone of the molecule.

TALTZ injection is a sterile, preservative free, clear and colorless to slightly yellow solution, for subcutaneous use available as 80 mg of ixekizumab in a 1 mL single-dose prefilled autoinjector or a single-dose prefilled syringe, 40 mg of ixekizumab in a 0.5 mL single-dose prefilled syringe, or 20 mg of ixekizumab in a 0.25 mL single-dose prefilled syringe. The prefilled autoinjector and prefilled syringe each contain a 1 mL glass syringe with a fixed 27 gauge ½ inch needle. The TALTZ 80 mg prefilled autoinjector and prefilled syringe are manufactured to deliver 80 mg of ixekizumab. The TALTZ 40 mg prefilled syringe is manufactured to deliver 40 mg of ixekizumab. The TALTZ 20 mg prefilled syringe is manufactured to deliver 20 mg of ixekizumab.

Each TALTZ 80 mg/mL single-dose autoinjector or TALTZ 80 mg/mL single-dose prefilled syringe is composed of ixekizumab (80 mg); Polysorbate 80, USP (0.3 mg); Sucrose, USP (80 mg); and Water for Injection, USP. Sodium Hydroxide, USP-NF, may have been added to adjust pH. The TALTZ solution has a pH of 5.2 – 6.2.

Each TALTZ 40 mg/0.5 mL single-dose prefilled syringe is composed of ixekizumab (40 mg); Polysorbate 80, USP (0.15 mg); Sucrose, USP (40 mg); and Water for Injection, USP. Sodium Hydroxide, USP-NF, may have been added to adjust pH. The TALTZ solution has a pH of 5.2 – 6.2.

Each TALTZ 20 mg/0.25 mL single-dose prefilled syringe is composed of ixekizumab (20 mg); Polysorbate 80, USP (0.08 mg); Sucrose, USP (20 mg); and Water for Injection, USP. Sodium Hydroxide, USP-NF, may have been added to adjust pH. The TALTZ solution has a pH of 5.2 – 6.2.

12 CLINICAL PHARMACOLOGY

12.1 Mechanism of Action

Ixekizumab is a humanized IgG4 monoclonal antibody that selectively binds with the interleukin 17A (IL-17A) cytokine and inhibits its interaction with the IL-17 receptor. IL-17A is a naturally occurring cytokine that is involved in normal inflammatory and immune responses. Ixekizumab inhibits the release of proinflammatory cytokines and chemokines.

12.2 Pharmacodynamics

No formal pharmacodynamic studies have been conducted with TALTZ.

12.3 Pharmacokinetics

The pharmacokinetic (PK) properties of ixekizumab were similar across the adult plaque psoriasis, psoriatic arthritis, ankylosing spondylitis, and non-radiographic axial spondyloarthritis indications.

Absorption

Following a single subcutaneous dose of 160 mg in subjects with plaque psoriasis, ixekizumab reached peak mean (±SD) serum concentrations (Cmax) of 16.2 ±6.6 mcg/mL by approximately 4 days post dose.

Steady-state concentrations were achieved by Week 8 following the 160 mg starting dose and 80 mg every 2 weeks dosing regimen; the mean ±SD steady-state trough concentration was 9.3 ±5.3 mcg/mL. Steady-state concentrations were achieved approximately 10 weeks after switching from the 80 mg every 2 weeks dosing regimen to the 80 mg every 4 weeks dosing regimen at Week 12. The mean ±SD steady-state trough concentration was 3.5 ±2.5 mcg/mL.

In studies of subjects with plaque psoriasis, ixekizumab bioavailability ranged from 60% to 81% following subcutaneous injection. Administration of ixekizumab via injection in the thigh achieved a higher bioavailability relative to that achieved using other injection sites including the arm and abdomen.

Distribution

The mean (geometric CV%) volume of distribution at steady-state was 7.11 L (29%) in subjects with plaque psoriasis.

Elimination

The metabolic pathway of ixekizumab has not been characterized. As a humanized IgG4 monoclonal antibody ixekizumab is expected to be degraded into small peptides and amino acids via catabolic pathways in the same manner as endogenous IgG.

The mean systemic clearance was 0.39 L/day (37%) and the mean (geometric CV%) half-life was 13 days (40%) in subjects with plaque psoriasis.

Weight

Ixekizumab clearance and volume of distribution increase as body weight increases.

Dose Linearity

Ixekizumab exhibited dose-proportional pharmacokinetics in subjects with plaque psoriasis over a dose range from 5 mg (not the recommended dose) to 160 mg following subcutaneous administration.

Specific Populations

Age:

Geriatric Population

Population pharmacokinetic analysis indicated that age did not significantly influence the clearance of ixekizumab in adult subjects with plaque psoriasis. Subjects who are 65 years or older had a similar ixekizumab clearance as compared to subjects less than 65 years old.

Pediatric Population

Pediatric psoriasis subjects (6 to less than 18 years of age) were administered ixekizumab at the recommended pediatric dosing regimen for 12 weeks. Subjects weighing >50 kg and 25 to 50 kg had a mean ±SD steady-state trough concentration of 3.8 ±2.2 mcg/mL and 3.9 ±2.4 mcg/mL at Week 12, respectively. There were limited PK data (n=2) in subjects weighing <25 kg at Week 12.

Drug Interaction Studies

Population PK data analyses indicated that the clearance of ixekizumab was not impacted by concomitant administration of methotrexate, or by prior exposure to methotrexate or adalimumab in patients with psoriatic arthritis.

Population PK data analyses indicated that the clearance of ixekizumab was not impacted by concomitant administration of oral corticosteroids, NSAIDs, or cDMARDs (sulfasalazine and methotrexate) in patients with ankylosing spondylitis and non-radiographic axial spondyloarthritis.

Cytochrome P450 Substrates

No clinically significant changes in exposure of caffeine (CYP1A2 substrate), warfarin (CYP2C9 substrate), omeprazole (CYP2C19 substrate) or midazolam (CYP3A substrate) were observed in subjects with plaque psoriasis when used concomitantly with a single 160 mg dose of ixekizumab, or multiple doses of 80 mg every 2 weeks. The potential effect of ixekizumab on the CYP2D6 activity cannot be ruled out due to high variability in exposure (approximately ±2-fold) of dextromethorphan and its CYP2D6 metabolite dextrorphan in psoriasis subjects.

13 NONCLINICAL TOXICOLOGY

13.1 Carcinogenesis, Mutagenesis, Impairment of Fertility

Animal studies have not been conducted to evaluate the carcinogenic or mutagenic potential of TALTZ. Moreover published literature is mixed on potential effects on malignancy risk due to the inhibition of IL-17A activity, the pharmacological action of TALTZ. Some published literature suggests that IL-17A directly promotes cancer cell invasion, suggesting a potential beneficial effect by TALTZ, whereas other reports indicate IL-17A promotes T-cell mediated tumor rejection, suggesting a potential adverse effect by TALTZ. However, neutralization of IL-17A with TALTZ has not been studied in these models. Depletion of IL-17A with a neutralizing antibody inhibited tumor development in mice, suggesting a potential beneficial effect by TALTZ. The relevance of experimental findings in mouse models for malignancy risk in humans is unknown.

No effects on fertility parameters such as reproductive organs, menstrual cycle length, or sperm analysis were observed in sexually mature cynomolgus monkeys that were administered ixekizumab for 13 weeks at a subcutaneous dose of 50 mg/kg/week (19 times the MRHD on a mg/kg basis). The monkeys were not mated to evaluate fertility.

14 CLINICAL STUDIES

14.1 Adult Plaque Psoriasis

Three multicenter, randomized, double-blind, placebo-controlled trials, Trials 1, 2, and 3 (NCT 01474512, NCT 01597245, NCT 01646177), enrolled a total of 3866 subjects 18 years of age and older with plaque psoriasis who had a minimum body surface area involvement of 10%, a static Physician Global Assessment (sPGA) score of ≥3 in the overall assessment (plaque thickness/induration, erythema, and scaling) of psoriasis on a severity scale of 0 to 5, a Psoriasis Area and Severity Index (PASI) score ≥12, and who were candidates for phototherapy or systemic therapy.

In all three trials, subjects were randomized to either placebo or TALTZ (80 mg every 2 weeks [Q2W]) for 12 weeks, following a 160 mg starting dose. In the two active comparator trials (Trials 2 and 3), subjects were also randomized to receive U.S. approved etanercept 50 mg twice weekly for 12 weeks.

All three trials assessed the changes from baseline to Week 12 in the two co-primary endpoints: 1) PASI 75, the proportion of subjects who achieved at least a 75% reduction in the PASI composite score that takes into consideration both the percentage of body surface area affected and the nature and severity of psoriatic changes (induration, erythema and scaling) within the affected regions, and 2) sPGA of “0” (clear) or “1” (minimal), the proportion of subjects with an sPGA 0 or 1 and at least a 2-point improvement.

Other evaluated outcomes included the proportion of subjects with an sPGA score of 0 (clear), a reduction of at least 90% in PASI (PASI 90), a reduction of 100% in PASI (PASI 100), and an improvement of itch severity as measured by a reduction of at least 4 points on an 11-point itch Numeric Rating Scale.

Subjects in all treatment groups had a median baseline PASI score ranging from approximately 17 to 18. Baseline sPGA score was severe or very severe in 51% of subjects in Trial 1, 50% in Trial 2, and 48% in Trial 3.

Of all subjects, 44% had received prior phototherapy, 49% had received prior conventional systemic therapy, and 26% had received prior biologic therapy for the treatment of psoriasis. Of the subjects who had received prior biologic therapy, 15% had received at least one anti-TNF alpha agent, and 9% had received an anti-IL 12/IL23. A total of 23% of study subjects had a history of psoriatic arthritis.

Clinical Response at Week 12

The results of Trials 1, 2, and 3 are presented in Table 3.

Table 3: Efficacy Results at Week 12 in Adults with Plaque Psoriasis in Trials 1, 2, and 3; NRIa
 | Trial 1 |  | Trial 2 |  | Trial 3
 | TALTZ 80 mgb Q2W (N=433) n (%) | Placebo (N=431) n (%) | TALTZ 80 mgb Q2W (N=351) n (%) | Placebo (N=168) n (%) | TALTZ 80 mgb Q2W (N=385) n (%) | Placebo (N=193) n (%)
sPGA of “0” (clear) or “1” (minimal) c | 354 (82) | 14 (3) | 292 (83) | 4 (2) | 310 (81) | 13 (7)
sPGA of “0” (clear) | 160 (37) | 0 | 147 (42) | 1 (1) | 155 (40) | 0
PASI 75 c | 386 (89) | 17 (4) | 315 (90) | 4 (2) | 336 (87) | 14 (7)
PASI 90 | 307 (71) | 2 (1) | 248 (71) | 1 (1) | 262 (68) | 6 (3)
PASI 100 | 153 (35) | 0 | 142 (40) | 1 (1) | 145 (38) | 0
Itch NRS (≥4 point improvement) d | 336 (86) | 58 (16) | 258 (85) | 19 (14) | 264 (83) | 33 (21)
a Abbreviations: N = number of patients in the intent-to-treat population; NRI = Non-Responder Imputation.
b At Week 0, subjects received 160 mg of TALTZ.
c Co-primary endpoints.
d Itch NRS (≥4 improvement) in subjects with baseline Itch NRS ≥4. The number of ITT subjects with baseline Itch NRS Score ≥4 are as follows: Trial 1, TALTZ n=391, PBO n=374; Trial 2, TALTZ n=303, PBO n=135; Trial 3, TALTZ n=320, PBO n=158.

Examination of age, gender, race, body weight, and previous treatment with a biologic did not identify differences in response to TALTZ among these subgroups at Week 12.

An integrated analysis of the U.S. sites in the two active comparator studies using U.S. approved etanercept, TALTZ demonstrated superiority to U.S. approved etanercept (50 mg twice weekly) on sPGA and PASI scores during the 12-week treatment period. The respective response rates for TALTZ 80 mg Q2W and U.S. approved etanercept 50 mg twice weekly were: sPGA of 0 or 1 (73% and 27%); PASI 75 (87% and 41%); sPGA of 0 (34% and 5%); PASI 90 (64% and 18%), and PASI 100 (34% and 4%).

Maintenance and Durability of Response

To evaluate the maintenance and durability of response, subjects originally randomized to TALTZ and who were responders at Week 12 (i.e., sPGA of 0 or 1) in Trial 1 and Trial 2 were re-randomized to an additional 48 weeks of either a maintenance dose of TALTZ 80 mg Q4W (every 4 weeks) or placebo. Non-responders (sPGA >1) at Week 12 and subjects who relapsed (sPGA ≥3) during the maintenance period were placed on TALTZ 80 mg Q4W.

For responders at Week 12, the percentage of subjects who maintained this response (sPGA 0 or 1) at Week 60 (48 weeks following re-randomization) in the integrated trials (Trial 1 and Trial 2) was higher for subjects treated with TALTZ 80 mg Q4W (75%) compared to those treated with placebo (7%).

For responders at Week 12 who were re-randomized to treatment withdrawal (i.e., placebo), the median time to relapse (sPGA ≥3) was 164 days in the integrated trials. Among these subjects, 66% regained a response of at least 0 or 1 on the sPGA within 12 weeks of restarting treatment with TALTZ 80 mg Q4W.

Psoriasis Involving the Genital Area

A randomized, double-blind, placebo-controlled trial (Trial 4) was conducted in 149 adult subjects with plaque psoriasis who had a minimum body surface area (BSA) involvement of 1%, a sPGA score of ≥3 (moderate psoriasis), a sPGA of Genitalia score of ≥3 (moderate psoriasis involving the genital area), who failed to respond to or were intolerant of at least one topical therapy used for treatment of psoriasis affecting the genital area, and who were candidates for phototherapy and/or systemic therapy.

Subjects had a median baseline PASI score of approximately 12. Baseline BSA involvement was at least 10% for approximately 60% of the enrolled subjects. Baseline sPGA of Genitalia score was severe or very severe in approximately 42% of the subjects; baseline sPGA score was severe or very severe in approximately 47% of the subjects.

Subjects randomized to TALTZ received an initial dose of 160 mg followed by 80 mg every 2 weeks for 12 weeks. The trial evaluated the primary endpoint of the proportion of subjects who achieved a “0” (clear) or “1” (minimal) response at Week 12 on sPGA of Genitalia. Other evaluated outcomes at Week 12 included the proportion of subjects who achieved a sPGA score of “0” (clear) or “1” (minimal), improvement of genital itch severity as measured by a reduction of at least 4 points in the 11-point Genital Psoriasis Symptoms Scale (GPSS) score Itch numeric rating scale (NRS), and the patient-perceived impact of psoriasis affecting the genital area on limiting frequency of sexual activity (intercourse or other activities) as measured by the Genital Psoriasis Sexual Frequency Questionnaire (GenPs-SFQ) Item 2 (In the past week how often did your genital psoriasis limit the frequency of your sexual activity?). SFQ Item 2 score ranges from 0 to 4 (0=never, 1=rarely, 2=sometimes, 3=often, 4=always); where higher scores indicate greater limitations on the frequency of sexual activity in the past week.

The results of Trial 4 are presented in Table 4.

Table 4: Efficacy Results at Week 12 in Adults with Genital Psoriasis in Trial 4; NRIa
Endpoints | TALTZ 80 mg Q2Wb n (%) | Placebo n (%)
Number of subjects randomized | N=75 | N=74
sPGA of Genitalia “0” (clear) or “1” (minimal) | 55 (73%) | 6 (8%)
sPGA “0” (clear) or “1” (minimal) | 55 (73%) | 2 (3%)
Number of subjects with baseline GPSSa Itch NRS Score ≥4 | N=56 | N=51
GPSS Genital Itch (≥4 point improvement) | 31 (55%) | 3 (6%)
Number of subjects with baseline GenPs-SFQa Item 2 Score ≥2 | N=37 | N=42
GenPs-SFQ Item 2 score “0” (never) or “1” (rarely) | 29 (78%) | 9 (21%)
a Abbreviations: NRI = Non-Responder Imputation; GPSS = Genital Psoriasis Symptoms Scale; GenPs-SFQ = Genital Psoriasis Sexual Frequency Questionnaire.
b At Week 0, subjects received 160 mg of TALTZ, followed by 80 mg every 2 weeks for 12 weeks.

14.2 Pediatric Plaque Psoriasis

A randomized, double-blind, multicenter, placebo-controlled trial (IXORA-Peds, NCT03073200) enrolled 171 pediatric subjects 6 to less than 18 years of age, with moderate-to-severe plaque psoriasis (as defined by a sPGA score ≥3, involving ≥10% of the body surface area, and a PASI score ≥12) who were candidates for phototherapy or systemic therapy or were inadequately controlled on topical therapy.

Subjects were randomized to placebo or TALTZ with dosing stratified by weight.

- <25 kg: 40 mg at Week 0 followed by 20 mg Q4W
- 25 kg to 50 kg: 80 mg at Week 0 followed by 40 mg Q4W
- >50 kg: 160 mg at Week 0 followed by 80 mg Q4W

Response to treatment was assessed at 12 weeks of therapy and was defined by the proportion of subjects who achieved an sPGA score of “0” (clear) or “1” (almost clear) with at least a 2-point improvement from baseline and the proportion of subjects that achieved a reduction in PASI score of at least 75% (PASI 75) from baseline.

Other evaluated outcomes included the proportion of subjects who achieved PASI 90, PASI 100, sPGA of “0” and an improvement of itch severity as measured by a reduction of at least 4 points on an 11-point itch Numeric Rating Scale.

Subjects had a median baseline PASI score of 17 (range 12-49). Baseline sPGA score was severe or very severe in 49%. Of all subjects, 22% had received prior phototherapy and 32% had received prior conventional systemic therapy for the treatment of psoriasis.

Clinical Response

The efficacy results of IXORA-Peds are presented in Table 5.

Table 5: Efficacy Results in Pediatric Subjects with Plaque Psoriasis in IXORA-Peds, NRIa
 | TALTZb (N=115) n (%) | Placebo (N=56) n (%)
Week 12
sPGA “0” (clear) or “1” (minimal) c | 93 (81%) | 6 (11%)
sPGA “0” (clear) | 60 (52%) | 1 (2%)
PASI 75 c | 102 (89%) | 14 (25%)
PASI 90 | 90 (78%) | 3 (5%)
PASI 100 | 57 (50%) | 1 (2%)
Itch NRS (≥4 point improvement) d | 59 (71%) | 8 (20%)
Week 4
sPGA “0” (clear) or “1” (minimal) | 55 (48%) | 4 (7%)
PASI 75 | 62 (54%) | 5 (9%)
a Abbreviations: N = Number of subjects in the intent-to-treat population; NRI = Non-Responder Imputation.
b At Week 0, subjects received 160 mg, 80 mg, or 40 mg of TALTZ, followed by 80 mg, 40 mg, or 20 mg every 4 weeks, depending on weight category, for 12 weeks.
c Co-primary endpoints.
d Itch NRS (≥4 improvement) in subjects with baseline Itch NRS ≥4. The number of ITT subjects with baseline Itch NRS Score ≥4 are as follows: TALTZ, n = 83; PBO, n = 40.

14.3 Psoriatic Arthritis

The safety and efficacy of TALTZ were assessed in 679 patients, in 2 randomized, double-blind, placebo-controlled studies (PsA1 and PsA2) in adult patients, age 18 years and older with active psoriatic arthritis (at least 3 swollen and at least 3 tender joints) despite non-steroidal anti-inflammatory drug (NSAID), corticosteroid or disease modifying anti-rheumatic drug (DMARD) therapy. Patients in these studies had a diagnosis of PsA for at least 6 months across both studies. At baseline, 60% and 23% of the patients had enthesitis and dactylitis, respectively. In PsA2, all patients discontinued previous treatment with anti-TNFα agents due to either inadequate response or intolerance. In addition, approximately 47% of patients from both studies had concomitant methotrexate (MTX) use.

PsA1 Study (NCT 01695239) evaluated 417 biologic-naive patients, who were treated with either TALTZ 160 mg at Week 0 followed by 80 mg every 2 weeks (Q2W) or 4 weeks (Q4W), adalimumab 40 mg every 2 weeks, or placebo. PsA2 Study (NCT 02349295) evaluated 363 anti-TNFα experienced patients, who were treated with TALTZ 160 mg at Week 0 followed by 80 mg every 2 or 4 weeks, or placebo. Patients receiving placebo were re-randomized to receive TALTZ (80 mg every 2 or 4 weeks) at Week 16 or Week 24 based on responder status. The primary endpoint was the percentage of patients achieving an ACR20 response at Week 24.

Clinical Response

In both studies, patients treated with TALTZ 80 mg Q4W demonstrated a greater clinical response including ACR20, ACR50, and ACR70 compared to placebo at Week 24 (Table 6). In PsA2, responses were seen regardless of prior anti-TNFα exposure.

Table 6: Responsesa at Week 12 and 24; NRIb
 | PsA1 – anti-TNFα naive |  |  | PsA2 – anti-TNFα – experienced
 | TALTZ 80 mgc Q4W (N=107) | Placebo (N=106) | Difference from placebo (95% CI) | TALTZ 80 mgc Q4W (N=122) | Placebo (N=118) | Difference from placebo (95% CI)
ACR20 response
Week 12 (%) | 57 | 31 | 26 (13, 39) | 50 | 22 | 28 (16, 40)
Week 24 (%) | 58 | 30 | 28 (15, 41) | 53 | 20 | 34 (22, 45)
ACR50 response
Week 12 (%) | 34 | 5 | 29 (19, 39) | 31 | 3 | 28 (19, 37)
Week 24 (%) | 40 | 15 | 25 (14, 37) | 35 | 5 | 30 (21, 40)
ACR70 response
Week 12 (%) | 15 | 0 | 15 (8, 22) | 15 | 2 | 13 (6, 20)
Week 24 (%) | 23 | 6 | 18 (9, 27) | 22 | 0 | 22 (15, 30)
a Patients who met escape criteria (less than 20% improvement in tender and swollen joint counts) at Week 16 or had missing data at Week 24 were considered non-responders at Week 24.
b Abbreviations: N = number of patients in the intent-to-treat population; NRI = Non-Responder Imputation.
c At Week 0, patients received 160 mg of TALTZ.

The percentage of patients achieving ACR20 response by visit is shown in Figure 1.

Figure 1: Percent of Patients Achieving ACR20 Responsea in PsA1 Through Week 24

a Patients who met escape criteria (less than 20% improvement in tender and swollen joint counts) at Week 16 or had missing data at Week 24 were considered non-responders at Week 24.

The improvements in the components of the ACR response criteria are shown in Table 7.

Table 7: Efficacy results in ACR Components at Week 12 and 16
 | PsA1 |  | PsA2
 | TALTZ 80 mga Q4W (N=107) | Placebo (N=106) | TALTZ 80 mga Q4W (N=122) | Placebo (N=118)
No. of Swollen Joints
Baseline | 11.4 | 10.6 | 13.1 | 10.3
Mean Change at Week 12 | -6.2 | -3.2 | -5.8 | -2.6
Mean Change at Week 16 | -6.2 | -3.0 | -7.4 | -2.6
No. of Tender Joints
Baseline | 20.5 | 19.2 | 22.0 | 23.0
Mean Change at Week 12 | -10.3 | -3.5 | -9.4 | -5.4
Mean Change at Week 16 | -9.7 | -4.0 | -10.1 | -3.0
Patient's Assessment of Pain
Baseline | 60.1 | 58.5 | 63.9 | 63.9
Mean Change at Week 12 | -26.6 | -9.1 | -29.8 | -11.9
Mean Change at Week 16 | -26.1 | -10.6 | -30.1 | -12.3
Patient Global Assessment
Baseline | 62.7 | 61.1 | 66.4 | 64.1
Mean Change at Week 12 | -29.7 | -11.1 | -34.5 | -10.7
Mean Change at Week 16 | -30.4 | -13.2 | -35.3 | -15.7
Physician Global Assessment
Baseline | 57.6 | 55.9 | 60.3 | 58.9
Mean Change at Week 12 | -34.0 | -16.6 | -34.4 | -15.9
Mean Change at Week 16 | -35.5 | -16.5 | -32.9 | -9.7
Disability Index (HAQ-DI) b
Baseline | 1.2 | 1.2 | 1.2 | 1.2
Mean Change at Week 12 | -0.4 | -0.1 | -0.4 | -0.1
Mean Change at Week 16 | -0.4 | -0.1 | -0.5 | -0.1
CRP (mg/L)
Baseline | 12.8 | 15.1 | 17.0 | 12.1
Mean Change at Week 12 | -8.8 | -3.2 | -11.4 | -4.3
Mean Change at Week 16 | -9.3 | -3.2 | -11.2 | -5.9
a At Week 0, subjects received 160 mg of TALTZ.
b Disability Index of the Health Assessment Questionnaire; 0 = best, 3 = worst, measures the patient's ability to perform the following: dress/groom, arise, eat, walk, reach, grip, maintain hygiene, and maintain daily activity.

Treatment with TALTZ resulted in improvement in dactylitis and enthesitis in patients with pre-existing dactylitis or enthesitis.

Treatment with TALTZ 80 mg Q4W resulted in an improvement in psoriatic skin lesions in patients with PsA.

Radiographic Response

Radiographic changes were assessed in PsA1. Inhibition of progression of structural damage was assessed radiographically and expressed as the change in modified total Sharp score (mTSS) at Week 16, compared to baseline. The total Sharp score was modified for psoriatic arthritis by addition of hand distal interphalangeal (DIP) joints.

TALTZ 80 mg Q4W inhibited the progression of structural joint damage (mTSS) compared to placebo at Week 16. The adjusted mean change from baseline in the mTSS was 0.13 for TALTZ 80 mg Q4W and 0.36 for placebo (difference in means TALTZ minus placebo: -0.23, 95% CI: (-0.42, -0.04)).

Physical Function

TALTZ treated patients showed improvement in physical function compared to patients treated with placebo as assessed by the Health Assessment Questionnaire-Disability Index (HAQ-DI) at Week 12 and 24. In both studies, the proportion of HAQ-DI responders (≥0.35 improvement in HAQ-DI score) was greater in the TALTZ 80 mg Q4W groups compared to placebo at week 12 and 24.

Other Health-Related Outcomes

General health status was assessed by the Short Form health survey (SF-36). At Week 12 in PsA1 and PsA2, patients treated with TALTZ showed greater improvement from baseline in the SF-36 physical component summary (PCS) score compared to patients treated with placebo but this improvement was not consistent in both studies for the SF-36 mental component summary (MCS) score. At Week 12, there was consistent evidence of effect in the physical-functioning, role-physical, bodily-pain, and general health domains but not in the social-functioning, role-emotional, vitality, and mental health domains.

14.4 Ankylosing Spondylitis

The safety and efficacy of TALTZ were assessed in 567 patients, in 2 randomized, double-blind, placebo-controlled studies (AS1 and AS2) in adult patients, age 18 years and older with active ankylosing spondylitis. Patients had active disease as defined by the Bath Ankylosing Spondylitis Disease Activity Index (BASDAI) ≥4 despite non-steroidal anti-inflammatory drug (NSAID), corticosteroid, or disease modifying anti-rheumatic drug (DMARD) therapy. At baseline, patients had symptoms of AS for an average of 17 years across both studies. At baseline, approximately 32% of the patients were on a concomitant cDMARD. In AS2, all patients discontinued previous treatment with 1 or 2 TNF inhibitors due to either inadequate response or intolerance.

AS1 Study (NCT 02696785) evaluated 341 biologic-naive patients, who were treated with either TALTZ 80 mg or 160 mg at Week 0 followed by 80 mg every 2 weeks (Q2W) or 4 weeks (Q4W), adalimumab 40 mg every 2 weeks, or with placebo. Patients receiving placebo were re-randomized at Week 16 to receive TALTZ (160 mg starting dose, followed by 80 mg Q2W or Q4W). Patients receiving adalimumab were re-randomized at Week 16 to receive TALTZ (80 mg Q2W or Q4W). AS2 Study (NCT 02696798) evaluated 316 TNF-inhibitor experienced patients (90% were inadequate responders and 10% were intolerant to TNF inhibitors). All patients were treated with TALTZ 80 or 160 mg at Week 0 followed by 80 mg Q2W or Q4W, or with placebo. Patients receiving placebo were re-randomized at Week 16 to receive TALTZ (160 mg initial dose, followed by 80 mg Q2W or Q4W). The primary endpoint in both studies was the percentage of patients achieving an Assessment of Spondyloarthritis International Society 40 (ASAS40) response at Week 16.

Clinical Response

In both studies, patients treated with TALTZ 80 mg Q4W demonstrated greater improvements in ASAS40 and ASAS20 responses compared to placebo at Week 16 (Table 8). Responses were seen regardless of concomitant therapies. In AS2, responses were seen regardless of prior TNF-inhibitor exposure.

Table 8: ASAS20 and ASAS40 Responses at Week 16, NRIa,b
 | AS1 – biologic-naive |  |  | AS2 – TNF-inhibitor experienced
 | TALTZ 80 mg Q4Wc (N=81) | Placebo (N=87) | Difference from placebo (95% CI) | TALTZ 80 mg Q4Wc (N=114) | Placebo (N=104) | Difference from placebo (95% CI)
ASAS20 responsed, % | 64 | 40 | 24 (9, 39) | 48 | 30 | 18 (6, 31)
ASAS40 responsed,e, % | 48 | 18 | 30 (16, 43) | 25 | 13 | 13 (3, 23)
a Abbreviations: N = number of patients in the intent-to-treat population; NRI = Non-responder Imputation.
b Patients with missing data were counted as non-responders.
c At Week 0, patients received 80 mg or 160 mg of TALTZ.
d An ASAS20 response is defined as a ≥20% improvement and an absolute improvement from baseline of ≥1 units (range 0 to 10) in ≥3 of 4 domains (Patient Global, Spinal Pain, Function, and Inflammation), and no worsening of ≥20% and ≥1 unit (range 0 to 10) in the remaining domain. An ASAS40 response is defined as a ≥40% improvement and an absolute improvement from baseline of ≥2 units in ≥3 of 4 domains without any worsening in the remaining domain.
e Primary endpoint.

The percent of patients achieving ASAS40 response by visit in AS1 is shown in Figure 2.

Figure 2: ASAS40 Response through Week 16, NRIa

a Patients with missing data were counted as non-responders.

The improvement in the main components of the ASAS40 response criteria and other measures of disease activity are shown in Table 9.

Table 9: ASAS Components and Other Measures of Disease Activity at Week 16a,b
 | AS1 – biologic-naive |  | AS2 – TNF-inhibitor experienced
 | TALTZ 80 mg Q4Wc (N=81) | Placebo (N=87) | TALTZ 80 mg Q4Wc (N=114) | Placebo (N=104)
ASAS Components
Patient Global Assessment (0-10)
Baseline | 6.9 | 7.1 | 8.0 | 7.8
Mean Change from Baseline | -2.5 | -1.4 | -2.4 | -0.7
Total Spinal Pain (0-10)
Baseline | 7.2 | 7.4 | 7.9 | 7.8
Mean Change from Baseline | -3.2 | -1.7 | -2.4 | -1.0
BASFI (0-10)
Baseline | 6.1 | 6.4 | 7.4 | 7.0
Mean Change from Baseline | -2.4 | -1.2 | -1.7 | -0.6
Inflammation (0-10)d
Baseline | 6.5 | 6.8 | 7.2 | 7.2
Mean Change from Baseline | -3.2 | -1.3 | -2.4 | -0.7
Other Measures of Disease Activity
BASDAI Score
Baseline | 6.8 | 6.8 | 7.5 | 7.3
Mean Change from Baseline | -2.9 | -1.4 | -2.2 | -0.9
BASMI
Baseline | 3.9 | 4.5 | 4.7 | 4.9
Mean Change from Baseline | -0.5 | -0.1 | -0.3 | -0.0
hsCRP (mg/L)
Baseline | 12.2 | 16.0 | 20.2 | 16.0
Mean Change from Baseline | -5.2 | 1.4 | -11.1 | 9.7
a Abbreviations: ASDAS = Ankylosing Spondylitis Disease Activity Score; BASDAI = Bath Ankylosing Spondylitis Disease Activity Index; BASFI = Bath Ankylosing Spondylitis Functional Index; BASMI = Bath Ankylosing Spondylitis Metrology Index; hsCRP = High sensitivity C-reactive protein.
b Mean changes are least-squares mean changes from baseline at Week 16.
c At Week 0, patients received 80 or 160 mg of TALTZ.
d Inflammation is the mean of patient-reported stiffness self-assessments (questions 5 and 6) in BASDAI.

Health-Related Outcomes

General health status and quality of life was assessed by the Short Form health survey (SF-36). At Week 16, in AS1 and AS2, compared to placebo, patients treated with TALTZ showed greater improvement from baseline in the SF-36 physical component summary (PCS) score and the physical functioning, role physical, bodily pain, vitality, and general health domains, with no consistent improvements in the mental component summary (MCS), social functioning, role emotional, and mental health domains.

14.5 Non-radiographic Axial Spondyloarthritis

The efficacy and safety of TALTZ were assessed in a randomized, double-blind, 52-week placebo-controlled study (nr-axSpA1) (NCT 02757352) in patients ≥18 years of age with active axial spondyloarthritis for at least 3 months. Patients must have had objective signs of inflammation indicated by elevated C-reactive protein (CRP) (defined as greater than 5 mg/L), and/or sacroiliitis on magnetic resonance imaging (MRI), and no definitive radiographic evidence of structural damage on sacroiliac joints. Patients had active disease as defined by the Bath Ankylosing Spondylitis Disease Activity Index (BASDAI) ≥4, and spinal pain ≥4 on a 0 to 10 Numerical Rating Scale (NRS). Patients must have been intolerant to or had an inadequate response to at least two NSAIDs. Patients were treated with either placebo or TALTZ 80 mg or 160 mg at Week 0, followed by either 80 mg every 2 weeks (Q2W) or 80 mg every 4 weeks (Q4W). Initiation and/or dose adjustment of concomitant medications (NSAIDs, cDMARDs, corticosteroids, analgesics) were permitted starting at Week 16. Patients were allowed to transition to use of open-label TALTZ 80 mg Q2W starting at Week 16 up to Week 44 at the discretion of the investigator.

At baseline, patients had symptoms of nr-axSpA for an average of 11 years. Approximately 39% of the patients were on a concomitant cDMARD.

The primary endpoint was the percentage of patients achieving an Assessment of Spondyloarthritis International Society 40 (ASAS40) response at Week 52. The ASAS40 response was also evaluated at Week 16 as a major secondary endpoint.

Clinical Response

At both Weeks 16 and 52, a greater proportion of patients treated with TALTZ 80 mg Q4W had ASAS40 response compared to patients treated with placebo (Table 10). The components of ASAS response criteria and CRP are shown in Table 11.

Table 10: ASAS40 Responses at Week 16 and Week 52, NRIa,b
 | Week 16 |  |  | Week 52
 | TALTZ 80 mg Q4Wc,d (N=96) | Placebo (N=105) | Difference from placebo (95% CI) | TALTZ 80 mg Q4Wc,d (N=96) | Placebo (N=105) | Difference from placebo (95% CI)
ASAS40 responsee, % | 35.4 | 19.0 | 16.4 (4.2, 28.5) | 30.2 | 13.3 | 16.9 (5.6, 28.1)
a Abbreviations: N = number of patients in the intent-to-treat population; NRI = Non-responder Imputation.
b Patients who initiated open-label TALTZ 80 mg Q2W, or discontinued initially randomized treatment and remained in the study, or were missing Week 16 or Week 52 data were counted as non-responders.
c Starting at Week 16 and up to Week 44, patients who were determined as inadequate responders by investigators were given the option to make changes in their background therapy and/or transition to open label TALTZ 80 mg Q2W.
d At Week 0, patients received 80 mg or 160 mg of TALTZ.
e An ASAS40 response is defined as a ≥40% improvement and an absolute improvement from baseline of ≥2 units in ≥3 of 4 domains without any worsening in the remaining domain.

The improvement in the main components of the ASAS40 response criteria and other measures of disease activity at Week 16 are shown in Table 11.

Table 11: ASAS Components and Other Measures of Disease Activity at Week 16a
 | TALTZ 80 mg Q4Wb (N=96) | Placebo (N=105)
ASAS Components
Patient Global Assessment (0-10)
Baseline | 7.1 | 7.4
Mean Change from Baselinec | -2.3 | -1.3
Total Spinal Pain (0-10)
Baseline | 7.3 | 7.4
Mean Change from Baselinec | -2.4 | -1.5
BASFI (0-10)
Baseline | 6.4 | 6.7
Mean Change from Baselinec | -2.0 | -1.3
Inflammation (0-10)d
Baseline | 6.8 | 7.0
Mean Change from Baselinec | -2.5 | -1.5
Other Measures of Disease Activity
BASDAI Score (0-10)
Baseline | 7.0 | 7.2
Mean Change from Baselinec | -2.2 | -1.5
BASMI (0-10)
Baseline | 3.2 | 3.2
Mean Change from Baselinec | -0.4 | -0.2
hsCRP (mg/L)
Baseline | 12.4 | 14.3
Mean Change from Baselinec | -8.0 | -3.0
a Abbreviations: BASDAI = Bath Ankylosing Spondylitis Disease Activity Index; BASFI = Bath Ankylosing Spondylitis Functional Index; BASMI = Bath Ankylosing Spondylitis Metrology Index; hsCRP = High sensitivity C-reactive protein; NRI = Non-responder Imputation.
b At Week 0, patients received 80 or 160 mg of TALTZ.
c Mean changes are least-squares mean changes from baseline at Week 16 using a mixed model for repeated measures adjusting for treatment group, screening MRI/CRP classification, visit, continuous baseline, interaction of visit with treatment, interaction of continuous baseline with visit.
d Inflammation is the mean of patient-reported stiffness self-assessments (questions 5 and 6) in BASDAI questionnaire.

The percent of patients achieving ASAS40 responses by visit is shown in Figure 3.

Figure 3: ASAS40 Responses through Week 16, NRIa

a Patients with missing data were counted as non-responders.

Health-Related Outcomes

General health status and quality of life was assessed by the Short Form health survey (SF-36). At Week 16, compared to placebo, nr-axSpA patients treated with TALTZ 80 mg Q4W showed greater improvement from baseline in the SF-36 physical component summary (PCS) score and physical functioning, bodily pain, vitality, and social functioning domains, with no consistent improvements in the mental component summary (MCS), role physical, general health, role emotional, and mental health domains.

16 HOW SUPPLIED/STORAGE AND HANDLING

How Supplied

TALTZ injection is a sterile, preservative free, clear and colorless to slightly yellow solution available in:

- a single-dose prefilled autoinjector or a single-dose prefilled syringe to deliver 80 mg ixekizumab.
- a single-dose prefilled syringe to deliver 40 mg ixekizumab.
- a single-dose prefilled syringe to deliver 20 mg ixekizumab.

TALTZ is supplied as:

 | Pack Size | NDC Code
Autoinjector
 | Carton of 1 | 0002-1445-11
80 mg single-dose | Carton of 2 | 0002-1445-27
 | Carton of 3 | 0002-1445-09
Prefilled syringe
80 mg single-dose | Carton of 1 | 0002-7724-11
40 mg single-dose | Carton of 1 | 0002-8905-11
20 mg single-dose | Carton of 1 | 0002-8900-11

Storage and Handling

TALTZ is sterile and preservative-free. Discard any unused portion.

- TALTZ must be protected from light until use.
- Store refrigerated at 2°C to 8°C (36°F to 46°F).
  - If needed, patients/caregivers may store TALTZ at room temperature up to 30°C (86°F) for up to 5 days in the original carton to protect from light. Once TALTZ has been stored at room temperature, do not return to the refrigerator and discard, if unused, within 5 days.
  - Record the date when TALTZ is first removed from the refrigerator in the spaces provided on the carton.
  - For the 2 or 3 autoinjector pack, remove a single autoinjector at a time leaving the remaining autoinjector(s) in the original carton in the refrigerator. Ensure the unrefrigerated TALTZ is protected from light.
- Do not freeze. Do not use TALTZ if it has been frozen.
- Do not shake.
- Discard the TALTZ single-dose autoinjector or syringe after use in a puncture-resistant container.
- Not made with natural rubber latex.

17 PATIENT COUNSELING INFORMATION

Advise the patient and/or caregiver to read the FDA-approved patient labeling (Medication Guide and Instructions for Use) before the patient starts using TALTZ, and each time the prescription is renewed, as there may be new information they need to know.

Instructions on Self-Administration: Provide guidance to patients and caregivers on proper subcutaneous injection technique, including aseptic technique, and how to use the autoinjector or prefilled syringe correctly [see Instructions for Use].

Infection: Inform patients that TALTZ may lower the ability of their immune system to fight infections, and that serious infections, including opportunistic infections, may occur with the use of TALTZ. Instruct patients of the importance of communicating any history of infections to the healthcare provider, and contacting their healthcare provider if they develop any symptoms of infection [see Warnings and Precautions (5.1)].

Allergic Reactions: Advise patients to seek immediate medical attention if they experience any symptoms of serious hypersensitivity reactions [see Warnings and Precautions (5.3)].

Eczematous Eruptions: Inform patients that skin reactions resembling eczema may occur with the use of TALTZ. Instruct patients to seek medical advice if they develop signs or symptoms of eczema [see Warnings and Precautions (5.4)].

Pregnancy: Advise patients that there is a pregnancy exposure registry that monitors pregnancy outcomes in women exposed to TALTZ during pregnancy. Advise patients to contact the registry at 1-800-284-1695 to enroll [see Use in Specific Populations (8.1)].

Eli Lilly and Company, Indianapolis, IN 46285, USA
US License Number 1891

Copyright © 2016, 2024, Eli Lilly and Company. All rights reserved.

TAL-0016-USPI-20240820

Medication Guide
TALTZ® (tolts)
(ixekizumab)
injection, for subcutaneous use

What is the most important information I should know about TALTZ?
TALTZ is a medicine that affects your immune system. TALTZ may lower the ability of your immune system to fight infections and may increase your risk of infections. Some people have had serious infections while taking TALTZ, including tuberculosis (TB), and infections caused by bacteria, fungi, or viruses that can spread throughout the body. Some people have been hospitalized from these infections.

- Your healthcare provider should check you for TB before you start treatment with TALTZ.
- Your healthcare provider may treat you with medicine for TB before you begin treatment with TALTZ if you have a past history of TB or have TB.
- Your healthcare provider should watch you closely for signs and symptoms of TB during and after treatment with TALTZ.

Before starting TALTZ, tell your healthcare provider if you:

- are being treated for an infection
- have an infection that does not go away or that keeps coming back
- have TB or have been in close contact with someone with TB
- think you have an infection or have symptoms of an infection such as:

- fever, sweats, or chills
- muscle aches
- cough
- shortness of breath
- blood in your phlegm (mucus)

- weight loss
- warm, red, or painful skin or sores on your body
- diarrhea or stomach pain
- burning when you urinate or urinate more often than normal

After starting TALTZ, call your healthcare provider right away if you have any of the symptoms of infection listed above.
Do not use TALTZ if you have any symptoms of infection unless you are instructed to by your healthcare provider.
See “What are the possible side effects of TALTZ?” for more information about side effects.

What is TALTZ?
TALTZ is a prescription medicine used to treat:

- people 6 years of age and older with moderate-to-severe plaque psoriasis who may benefit from taking injections or pills (systemic therapy) or phototherapy (treatment using ultraviolet or UV light).
- adults with active psoriatic arthritis. TALTZ can be used alone or with the medicine methotrexate.
- adults with active ankylosing spondylitis.
- adults with active non-radiographic axial spondyloarthritis with objective signs of inflammation.

It is not known if TALTZ is safe and effective in children for conditions other than plaque psoriasis or in children under 6 years of age.

Do not use TALTZ if you have had a severe allergic reaction to ixekizumab or any of the other ingredients in TALTZ.
See the end of this Medication Guide for a complete list of ingredients in TALTZ.

Before using TALTZ, tell your healthcare provider about all of your medical conditions, including if you:

- have any of the conditions or symptoms listed in the section “What is the most important information I should know about TALTZ?”
- have Crohn's disease or ulcerative colitis
- have recently received or are scheduled to receive an immunization (vaccine). You should avoid receiving live vaccines during treatment with TALTZ.
- are pregnant or plan to become pregnant. It is not known if TALTZ can harm your unborn baby.
  Pregnancy Exposure Registry: There is a pregnancy registry to collect information about women who are exposed to TALTZ during pregnancy. The purpose of this registry is to collect information about the health of you and your baby. If you become pregnant while taking TALTZ, you are encouraged to enroll in the pregnancy registry by calling 1-800-284-1695 or by visiting online at www.pregnancyregistry.lilly.com.
- are breastfeeding or plan to breastfeed. It is not known if TALTZ passes into your breast milk.

Tell your healthcare provider about all the medicines you take, including prescription and over-the-counter medicines, vitamins, and herbal supplements.

How should I use TALTZ?
See the detailed “Instructions for Use” that comes with your TALTZ for information on how to prepare and inject a dose of TALTZ, and how to properly throw away (dispose of) used TALTZ autoinjectors and prefilled syringes.

- Use TALTZ exactly as prescribed by your or your child's healthcare provider.
- For children 6 to 17 years of age:
  - Your child's healthcare provider will decide which dose of TALTZ is right for your child and if you can give TALTZ to your child at home.
  - If your child's healthcare provider decides that you may give TALTZ injections at home, you should receive training on the right way to prepare and inject TALTZ. Do not try to give TALTZ to your child until you have been shown how to inject TALTZ.
  - Children should not inject themselves with TALTZ. You or an adult caregiver should prepare and give TALTZ injections to your child.
  - Children will be given a TALTZ injection every 4 weeks.
- For adults, if your healthcare provider decides that you or a caregiver may give your TALTZ injections at home, you should receive training on the right way to prepare and inject TALTZ. Do not try to inject TALTZ yourself, until you or your caregiver have been shown how to inject TALTZ.
- TALTZ comes in a single-dose autoinjector and single-dose prefilled syringes that you or your caregiver may use at home to give injections. Your or your child's healthcare provider will decide which type of TALTZ is best to use at home.
- TALTZ is given as an injection under the skin (subcutaneous injection), in the thighs or stomach area (abdomen) by you or a caregiver. A caregiver may also give the injection of TALTZ in the back of the arm.
- Do not give an injection in an area of the skin that is tender, bruised, red or hard, or in an area of skin that is affected by psoriasis.
- Each TALTZ injection should be given at a different site. Do not use the 1 inch area around your navel (belly button).

If you or your child forget to take a dose of TALTZ:

- Do not miss any doses of TALTZ unless your or your child's healthcare provider says it is okay. If you forget to take or give the TALTZ dose, inject a dose as soon as you remember. Then, take or give the next dose at the regular scheduled time.
- If you inject more TALTZ than prescribed, call your or your child's healthcare provider or go to the nearest emergency room right away.

What are the possible side effects of TALTZ?
TALTZ may cause serious side effects, including:

- See “What is the most important information I should know about TALTZ?”
- Serious allergic reactions. If you have a severe allergic reaction, do not give another injection of TALTZ. Get emergency medical help right away if you get any of the following symptoms of a serious allergic reaction:

- feel faint
- swelling of your face, eyelids, lips, mouth, tongue, or throat

- trouble breathing or throat tightness
- chest tightness
- skin rash

- Severe skin reactions that look like eczema can happen during treatment with TALTZ from days to months after your first dose and can sometimes lead to hospitalization. Your healthcare provider may temporarily stop treatment with TALTZ if you develop severe skin reactions. Tell your healthcare provider if you have any of the following signs or symptoms:

- redness or rash
- itching
- patches

- your skin is dry or feels like leather
- blisters or erosions that ooze or become crusty
- small bumps or plaques with scale or crusting

- Crohn's disease or ulcerative colitis (inflammatory bowel disease) can happen during treatment with TALTZ, including worsening symptoms. Tell your healthcare provider if you have new or worsening symptoms of inflammatory bowel disease during treatment with TALTZ, including:
  - stomach (abdomen) pain
  - diarrhea with or without blood
  - weight loss

- The most common side effects of TALTZ in adults and children include:

- injection site reactions
- upper respiratory infections

- nausea
- fungal infections

These are not all of the possible side effects of TALTZ. Tell your healthcare provider about any side effect that bothers you or that does not go away. Call your doctor for medical advice about side effects. You may report side effects to FDA at 1-800-FDA-1088.

How should I store TALTZ?

- Protect TALTZ from light.
- Store TALTZ in the refrigerator between 36°F to 46°F (2°C to 8°C).
  - If needed, you or a caregiver may store TALTZ at room temperature up to 86°F (30°C) for up to 5 days in the original carton to protect from light. Once TALTZ has been stored at room temperature, do not return to the refrigerator. Throw away TALTZ if it is not used within 5 days at room temperature.
  - Record the date when TALTZ is first removed from the refrigerator in the spaces provided on the carton.
  - For the 2 or 3 autoinjector pack, remove a single autoinjector at a time leaving the remaining autoinjector(s) in the original carton in the refrigerator. Make sure the unrefrigerated TALTZ is protected from light.
- Do not freeze TALTZ. Do not use if TALTZ has been frozen.
- Do not shake TALTZ.

Keep TALTZ and all medicines out of the reach of children.

General information about the safe and effective use of TALTZ.
Medicines are sometimes prescribed for purposes other than those listed in a Medication Guide. Do not use TALTZ for a condition for which it was not prescribed. Do not give TALTZ to other people, even if they have the same symptoms you have. It may harm them. You can ask your healthcare provider or pharmacist for information about TALTZ that is written for health professionals.

What are the ingredients in TALTZ?
Active ingredient: ixekizumab
Inactive ingredients: Polysorbate 80, Sucrose, and Water for Injection. Sodium Hydroxide may have been added to adjust pH.
Not made with natural rubber latex.
For more information about TALTZ, call 1-800-545-5979 (1-800-LillyRx) or go to the following website: www.taltz.com.
TALTZ® (ixekizumab) injection is a registered trademark of Eli Lilly and Company.
Eli Lilly and Company Indianapolis, IN 46285, USA, US License Number 1891
Copyright © 2016, 2024, Eli Lilly and Company. All rights reserved.
TAL-0011-MG-20240820

This Medication Guide has been approved by the U.S. Food and Drug Administration.

Revised: 08/2024

TALTZ 80 mg Autoinjector

INSTRUCTIONS FOR USE

TALTZ® [tol-t-s]
(ixekizumab)
injection, for subcutaneous use
Autoinjector

This Instructions for Use contains information on how to inject TALTZ.

Important Information You Need to Know Before Injecting TALTZ

- Your healthcare provider or nurse should show you how to prepare and inject TALTZ using the autoinjector. Do not inject yourself or someone else until you have been shown how to inject TALTZ.

- You and your caregiver should read this Instructions for Use before you start using TALTZ and each time you get a refill. Keep the Instructions for Use and refer to them as needed.

- Each TALTZ autoinjector contains 1 dose of TALTZ. The autoinjector is for one-time use only.

- The autoinjector contains glass parts. Handle autoinjector carefully. If you drop it on a hard surface, do not use it. Use a new TALTZ autoinjector for your injection.

- Your healthcare provider may help you decide where on your body to inject your dose. Do not give an injection in an area of the skin that is tender, bruised, red or hard, or in an area of skin that is affected by psoriasis. Read the “Choose your injection site” section of these instructions to help you choose which area can work best for you.

- If you have vision or hearing problems, do not use TALTZ autoinjector without help from a caregiver.

INSTRUCTIONS FOR USE
Before you use the TALTZ autoinjector, read and carefully follow all the step-by-step instructions.
Parts of the TALTZ autoinjector
Step 1 | Preparing to Inject TALTZ
Step 1a | - Take the TALTZ autoinjector from the refrigerator. - Remove the autoinjector from the package. Put the original package with any unused autoinjectors back in the refrigerator. - Leave the base cap on until you are ready to inject. - Wait 30 minutes to let the autoinjector warm to room temperature before you use it. - Do not microwave the autoinjector, run hot water over it, or leave it in direct sunlight. - Do not shake the autoinjector.

Step 1b | Gather the supplies needed for your injection:; - 1 alcohol wipe - 1 cotton ball or piece of gauze - 1 sharps disposal container. See “Disposing of TALTZ.”
Step 1c | Figure A | Inspect the autoinjector.; - Make sure the name TALTZ appears on the label. - The medicine inside should be clear. Its color may be colorless to slightly yellow.; Do not use the autoinjector, and dispose of as directed by your healthcare provider or pharmacist if:; - the expiration date printed on the label has passed (see Figure A). - it looks damaged. - the medicine is frozen. - the medicine is cloudy, discolored, or has small particles. The medicine should look clear and colorless to slightly yellow.
Step 1d | Wash your hands with soap and water before you inject TALTZ.
Step 1e | Figure B | Choose your injection site.; You may inject in your stomach area (abdomen) or in your thigh, or in the back of your arm (see Figure B). To inject in your arm, you will need someone to help you. Do not give an injection into areas where the skin is tender, bruised, red or hard, or in an area of skin that is affected by psoriasis. Do not inject within 1 inch of the navel (belly button). Alternate your injection sites.; - Do not inject in the exact same spot every time. For example, if your last injection was in your left thigh, your next injection should be in your right thigh, your abdomen, or the back of either arm. - Talk with your healthcare provider about where on your body to best inject TALTZ.
Step 1f | Prepare your skin. Clean your injection site with an alcohol wipe. Let the injection site dry before you inject TALTZ.

Step 2 |  | Injecting TALTZ
Step 2a |  | Figure C |  | Make sure the lock ring is in the lock position.; - Leave the base cap on until you are ready to inject. - Do not touch the needle.; Twist off the base cap in the direction of the arrows (see Figure C).; - Throw the base cap in the trash. You will not need to put the base cap back on. If you do, you could damage the needle or stick yourself by accident.
Step 2b |  | Figure D |  | Place the clear base flat and firmly against your skin at the injection site (see Figure D).
Step 2b |  |  |  | Place the clear base flat and firmly against your skin at the injection site (see Figure D).
Step 2c |  | Figure E |  | While holding the clear base against your skin, turn the lock ring to the unlock position (see Figure E). You are now ready to inject.
Step 2d |  | Figure F |  | Press the green injection button. There will be a loud click (see Figure F).; - Keep holding the clear base firmly against your skin. - You will hear a second click in about 10 seconds after the first one. The second click tells you that your injection is complete. - You will see the gray plunger at the top of the clear base.; Remove the autoinjector from your skin.; - Press a cotton ball or gauze over the injection site. Do not rub the injection site, as this may cause bruising. You may have slight bleeding. This is normal.; Do not put the base cap back on the autoinjector.
Step 3 |  | Disposing of TALTZ
Step 3a |  | Figure G
- Put the used TALTZ autoinjector in an FDA-cleared sharps disposal container right away after use (see Figure G). Do not throw away (dispose of) the TALTZ autoinjector in your household trash.
- If you do not have an FDA-cleared sharps disposal container, you may use a household container that is:
  - made of a heavy-duty plastic,
  - can be closed with a tight-fitting, puncture-resistant lid, without sharps being able to come out,
  - upright and stable during use,
  - leak-resistant, and
  - properly labeled to warn of hazardous waste inside the container.
- When your sharps disposal container is almost full, you will need to follow your community guidelines for the right way to dispose of your sharps disposal container. There may be state or local laws about how you should throw away needles and syringes. For more information about safe sharps disposal, and for specific information about sharps disposal in the state you live in, go to the FDA's website at: http://www.fda.gov/safesharpsdisposal
- Do not recycle your used sharps disposal container.

Commonly asked questions and answers.
Q. | What if I see bubbles in the TALTZ autoinjector?
A. | It is normal to have air bubbles in the autoinjector.
Q. | What if there is a drop of liquid on the tip of the needle when I remove the base cap?
A. | It is okay to see a drop of liquid on the tip of the needle.
Q. | What if I unlocked the autoinjector and pressed the green injection button before I twisted off the base cap?
A. | Do not remove the base cap. Dispose of the autoinjector and get a new one.
Q. | Do I need to hold the injection button down until the injection is complete?
A. | You do not need to hold the injection button down, but it may help you keep the autoinjector steady and firm against your skin.
Q. | What if the needle did not retract after my injection or I am not sure that the autoinjector worked in the right way?
A. | Do not touch the needle or replace the base cap. Store the autoinjector in a safe place (e.g., a household container as described in “Disposing of TALTZ”) to avoid an accidental needlestick and contact Lilly (1-800-545-5979) for instructions on how to return the autoinjector.
Q. | What if I hear more than 2 clicks during my injection? Did I get my complete dose?
A. | You may hear a soft click right before the second loud click. This is the normal operation of the autoinjector. Do not remove the autoinjector from your skin until you hear the second loud click.
Q. | How can I tell if my injection is complete?
A. | After you press the green injection button, you will hear 2 loud clicks. The second click tells you that your injection is complete. You will also see the gray plunger at the top of the clear base.
Q. | What if the autoinjector is left at room temperature for longer than 30 minutes?
A. | If needed, the autoinjector may be left out of the refrigerator at room temperature up to 86°F (30°C) for up to 5 days if protected from light. Throw away TALTZ if not used within the 5-day period at room temperature. See "Storing TALTZ" for more detail.
If you have more questions about how to use the TALTZ autoinjector:
 | - Call your healthcare provider - Call Lilly at 1-800-545-5979 (1-800-Lilly-Rx) - Visit www.taltz.com

Storing TALTZ

- Protect TALTZ from light.

- Store TALTZ in the refrigerator between 36°F to 46°F (2°C to 8°C).
  - If needed, you or a caregiver may store TALTZ at room temperature up to 86°F (30°C) for up to 5 days in the original carton to protect from light. Once TALTZ has been stored at room temperature, do not return to the refrigerator. Throw away TALTZ if it is not used within 5 days at room temperature.
  - Record the date when TALTZ is first removed from the refrigerator in the spaces provided on the carton.
  - For the 2 or 3 autoinjector pack, remove a single autoinjector at a time leaving the remaining autoinjector(s) in the original carton in the refrigerator. Ensure the unrefrigerated TALTZ is protected from light.

- Do not freeze TALTZ. Do not use if TALTZ has been frozen.

- Do not shake TALTZ.

Keep TALTZ and all medicines out of the reach of children.

Read the full Prescribing Information and Medication Guide for TALTZ inside this box to learn more about your medicine.

Eli Lilly and Company
Indianapolis, IN 46285, USA
US License Number 1891
TALTZ is a trademark of Eli Lilly and Company.
Copyright © 2016, 2023, Eli Lilly and Company. All rights reserved.
The TALTZ autoinjector meets the current dose accuracy and functional requirements of ISO 11608-1 and 11608-5.
This Instructions for Use has been approved by the U.S. Food and Drug Administration.
Revised: December 2023
TALAI-0008-IFU-20231218

TALTZ 80 mg Prefilled Syringe

INSTRUCTIONS FOR USE

TALTZ® (tol(t)s)
(ixekizumab)
injection, for subcutaneous use
Prefilled Syringe

Before you use the TALTZ prefilled syringe, read and carefully follow all the step-by-step instructions.

Important information:

- Your healthcare provider or nurse should show you how to prepare and inject TALTZ using the prefilled syringe. Do not inject yourself or someone else until you have been shown how to inject TALTZ.

- You and your caregiver should read this Instructions for Use before you start using TALTZ and each time you get a refill. Keep the Instructions for Use and refer to them as needed.

- Each TALTZ prefilled syringe contains 1 dose of TALTZ. The syringe is for one-time use only. Do not share or reuse your TALTZ prefilled syringe. You may give or get an infection.

- Your healthcare provider may help you decide where on your body to inject your dose. Do not give an injection in an area of the skin that is tender, bruised, red or hard, or in an area of skin that is affected by psoriasis. Read the “Choose your injection site” section of these instructions to help you choose which area can work best for you.

- If you have vision problems, do not use TALTZ prefilled syringe without help from a caregiver.

INSTRUCTIONS FOR USE
Before you use the TALTZ prefilled syringe, read and carefully follow all the step-by-step instructions.
Parts of the TALTZ prefilled syringe
1 | Get Ready
1a | - Take the TALTZ prefilled syringe from the refrigerator. - Remove the prefilled syringe from the package. Put the original package with any unused syringes back in the refrigerator. - Leave the needle cap on the syringe until you are ready to inject. - Wait 30 minutes to let the prefilled syringe warm to room temperature before you use it. - Do not microwave the syringe, run hot water over it, or leave it in direct sunlight. - Do not shake the prefilled syringe.
1b | Gather the supplies needed for your injection:; - 1 alcohol wipe - 1 cotton ball or piece of gauze - 1 sharps disposal container. See “Dispose of the used prefilled syringe.”
1c |  | Inspect the syringe. Leave the needle cap on the syringe until you are ready to inject.; - Make sure the name TALTZ appears on the label. - The medicine inside should be clear. Its color may be colorless to slightly yellow.; Do not use the prefilled syringe, and dispose of as directed by your healthcare provider or pharmacist if:; - the expiration date printed on the label has passed. - it looks damaged. - the medicine is frozen. - the medicine is cloudy, discolored, or has small particles. The medicine should look clear and colorless to slightly yellow.
1d | Wash your hands with soap and water before you inject TALTZ.
1e |  | Choose your injection site.; You may inject in your stomach area (abdomen) or in your thigh, or in the back of your arm. To inject in your arm, you will need someone to help you. Do not give an injection into areas where the skin is tender, bruised, red or hard, or in an area of skin that is affected by psoriasis. Do not inject within 1 inch of the navel (belly button). Alternate your injection sites.; - Do not inject in the exact same spot every time. For example, if your last injection was in your left thigh, your next injection should be in your right thigh, your abdomen, or the back of either arm. - Talk with your healthcare provider about where on your body to best inject TALTZ.
1f | Prepare your skin. Clean your injection site with an alcohol wipe. Let the injection site dry before you inject TALTZ.
2 | Inject TALTZ
2a |  | Pull the needle cap off and throw it away.; - Do not put the needle cap back on. You could damage the needle or stick yourself by accident. - Do not touch the needle.
2b |  | Gently pinch and hold a fold of skin where you will inject.
2c |  | Insert the needle at a 45-degree angle. Then gently let go of your skin. Make sure to keep the needle in place.; Let go of your skin before you push the plunger in.
2d |  | Push in the plunger.; - Slowly push on the thumb pad to push the plunger all the way in until all the medicine is injected. - The gray syringe plunger should be pushed all the way to the needle end of the syringe. - You should see the green plunger rod show through the syringe body when the injection is complete. - Gently remove the needle from your skin. - Press a cotton ball or gauze over the injection site. Do not rub the injection site, as this may cause bruising. You may have slight bleeding. This is normal.; Do not put the needle cap back on the prefilled syringe.
3 | Dispose of (throw away) the used prefilled syringe.
3a
- Put the used TALTZ prefilled syringe in a FDA-cleared sharps disposal container right away after use. Do not throw away (dispose of) the TALTZ prefilled syringe in your household trash.
- If you do not have a FDA-cleared sharps disposal container, you may use a household container that is:
  - made of a heavy-duty plastic,
  - can be closed with a tight-fitting, puncture-resistant lid, without sharps being able to come out,
  - upright and stable during use,
  - leak-resistant, and
  - properly labeled to warn of hazardous waste inside the container.
- When your sharps disposal container is almost full, you will need to follow your community guidelines for the right way to dispose of your sharps disposal container. There may be state or local laws about how you should throw away needles and syringes. For more information about safe sharps disposal, and for specific information about sharps disposal in the state you live in, go to the FDA's website at: http://www.fda.gov/safesharpsdisposal
- Do not recycle your used sharps disposal container.
Commonly asked questions and answers.
Q. | What if I see air bubbles in my TALTZ prefilled syringe?
A. | It is normal to have air bubbles in the prefilled syringe.
Q. | What if there is a drop of liquid on the tip of the needle when I remove the needle cap?
A. | It is okay to see a drop of liquid on the tip of the needle.
Q. | What if I cannot push in the plunger?
A. | If the plunger is stuck or damaged:
 | - Do not continue to use the syringe
 | - Remove the needle from your skin
 | - Dispose of the syringe and get a new one
Q. | How can I tell if my injection is complete?
A. | When your injection is complete:
 | - The green plunger rod should show through the body of the syringe.
 | - The gray syringe plunger should be pushed all the way to the needle end of the syringe.
Q. | What if the syringe is left at room temperature for longer than 30 minutes?
A. | If needed, the syringe may be left out of the refrigerator at room temperature up to 86°F (30°C) for up to 5 days if protected from light. Throw away TALTZ if not used within the 5-day period at room temperature. See "How should I store TALTZ prefilled syringe?" for more detail.
If you have more questions about how to use the TALTZ prefilled syringe:
- Call your healthcare provider
- Call Lilly at 1-800-545-5979 (1-800-Lilly-Rx)
- Visit www.taltz.com
How should I store TALTZ prefilled syringe?
- Protect TALTZ from light.
- Store TALTZ in the refrigerator between 36°F to 46°F (2°C to 8°C).
  - If needed, you or a caregiver may store TALTZ at room temperature up to 86°F (30°C) for up to 5 days in the original carton to protect from light. Once TALTZ has been stored at room temperature, do not return to the refrigerator. Throw away TALTZ if it is not used within 5 days at room temperature.
  - Record the date when TALTZ is first removed from the refrigerator in the spaces provided on the carton.
- Do not freeze TALTZ. Do not use if TALTZ has been frozen.
- Do not shake TALTZ.
Keep TALTZ and all medicines out of the reach of children.
Read the full Prescribing Information and Medication Guide for TALTZ inside this box to learn more about your medicine.
This Instructions for Use has been approved by the U.S. Food and Drug Administration.
Eli Lilly and Company
Indianapolis, IN 46285, USA
US License Number 1891
TALTZ is a trademark of Eli Lilly and Company.
Copyright © 2016, 2021, Eli Lilly and Company. All rights reserved.
TALPFS-0005-IFU-20210622
Revised: June 2021

TALTZ 40 mg Prefilled Syringe

INSTRUCTIONS FOR USE

TALTZ® [tol-t-s]
(ixekizumab)
injection, for subcutaneous use
40 mg/0.5 mL single-dose prefilled syringe

This Instructions for Use contains information on how to inject TALTZ.

Important Information You Need to Know Before Giving TALTZ Injection to Your Child

- Your child's healthcare provider or nurse should show you how to prepare and inject TALTZ using the prefilled syringe. Do not give the TALTZ prefilled syringe to your child until you have been shown how to inject TALTZ.
- Children 6 to 17 years of age should not inject themselves with TALTZ. You or an adult caregiver should prepare and give TALTZ injections to your child.
- You should read this Instructions for Use before injecting TALTZ and each time your child gets a refill. Keep the Instructions for Use and refer to them as needed.
- Each TALTZ prefilled syringe contains 1 dose (40 mg) of TALTZ. The syringe is for one-time use only. Do not share or reuse the TALTZ prefilled syringe. Your child may give or get an infection.
- Your child's healthcare provider may help you decide where on the body to inject the dose. Do not give an injection in an area of the skin that is tender, bruised, red or hard, or in an area of skin that is affected by psoriasis. Read the “Choose the injection site” section of these instructions to help you choose which area can work best.
- If you have vision problems, do not use TALTZ prefilled syringe without help.

Before you use the TALTZ prefilled syringe, read and carefully follow all the step-by-step instructions.
Parts of the TALTZ prefilled syringe
Step 1 | Preparing to Inject TALTZ
Step 1a | - Take the TALTZ prefilled syringe from the refrigerator. - Remove the prefilled syringe from the package. - Leave the needle cap on the syringe until you are ready to inject. - Wait 30 minutes to let the prefilled syringe warm to room temperature before you use it. - Do not microwave the syringe, run hot water over it, or leave it in direct sunlight. - Do not shake the prefilled syringe.
Step 1b | Gather the supplies needed for injection:; - 1 alcohol wipe - 1 cotton ball or piece of gauze - 1 sharps disposal container. See “Disposing of TALTZ”
Step 1c |  | Inspect the syringe. Leave the needle cap on the syringe until you are ready to inject.; - Make sure the name TALTZ appears on the label. - The medicine inside should be clear. Its color may be colorless to slightly yellow.; Do not use the prefilled syringe, and dispose of as directed by your child's healthcare provider or pharmacist if:; - the expiration date printed on the label has passed (see Figure A). - it looks damaged. - the medicine is frozen. - the medicine is cloudy, discolored, or has small particles. The medicine should look clear and colorless to slightly yellow.
Step 1d | Wash your hands with soap and water before you inject TALTZ.
Step 1e |  | Choose the injection site.; You may inject in the stomach area (abdomen) or in the thigh, or in the back of the arm (see Figure B). Do not give an injection into areas where the skin is tender, bruised, red or hard, or in an area of skin that is affected by psoriasis. Do not inject within 1 inch of the navel (belly button). Change (alternate) injection sites.; - Do not inject in the exact same spot every time. For example, if the last injection was in the left thigh, the next injection should be in the right thigh, the abdomen, or the back of either arm. - Talk with your child's healthcare provider about where on the body to best inject TALTZ.
Step 1f | Prepare the skin. Clean the injection site with an alcohol wipe. Let the injection site dry before you inject TALTZ.
Step 2 | Injecting TALTZ
Step 2a |  | Pull the needle cap off and throw it away (see Figure C).; - Do not put the needle cap back on. You could damage the needle or stick yourself by accident. - Do not touch the needle.
Step 2b |  | Gently pinch and hold a fold of skin where you will inject (see Figure D).
Step 2c |  | Insert the needle at a 45-degree angle to inject under the skin (subcutaneous injection) (see Figure E). Then gently let go of the skin. Make sure to keep the needle in place.; Let go of the skin before you push the plunger in (see Figure F).
Step 2d |  | Push in the plunger.; - Slowly push on the thumb pad to push the plunger all the way in until all the medicine is injected (see Figure G). - The gray syringe plunger should be pushed all the way to the needle end of the syringe. - You should see the gray syringe plunger at the bottom of the syringe body when the injection is complete (see Figure H). - Gently remove the needle from the skin. - Press a cotton ball or gauze over the injection site. Do not rub the injection site, as this may cause bruising. There may be slight bleeding. This is normal.; Do not put the needle cap back on the prefilled syringe.
Step 3 | Disposing of TALTZ
Step 3a
- Put the used TALTZ prefilled syringe in an FDA-cleared sharps disposal container right away after use (see Figure I). Do not throw away (dispose of) the TALTZ prefilled syringe in your household trash.
- If you do not have an FDA-cleared sharps disposal container, you may use a household container that is:
  - made of a heavy-duty plastic,
  - can be closed with a tight-fitting, puncture-resistant lid, without sharps being able to come out,
  - upright and stable during use,
  - leak-resistant, and
  - properly labeled to warn of hazardous waste inside the container.
- When your sharps disposal container is almost full, you will need to follow your community guidelines for the right way to dispose of your sharps disposal container. There may be state or local laws about how you should throw away needles and syringes. For more information about safe sharps disposal, and for specific information about sharps disposal in the state you live in, go to the FDA's website at: http://www.fda.gov/safesharpsdisposal
- Do not recycle your used sharps disposal container.
Commonly asked questions and answers.
Q. | What if I see air bubbles in the TALTZ prefilled syringe?
A. | It is normal to have air bubbles in the prefilled syringe.
Q. | What if there is a drop of liquid on the tip of the needle when I remove the needle cap?
A. | It is okay to see a drop of liquid on the tip of the needle.
Q. | What if I cannot push in the plunger?
A. | If the plunger is stuck or damaged:
 | - Do not continue to use the syringe
 | - Remove the needle from the skin
 | - Dispose of the syringe and get a new one
Q. | How can I tell if the injection is complete?
A. | When the injection is complete:
 | - The gray syringe plunger should be pushed all the way to the needle end of the syringe.
Q. | What if the syringe is left at room temperature for longer than 30 minutes?
A. | If needed, the syringe may be left out of the refrigerator at room temperature up to 86°F (30°C) for up to 5 days if protected from light. Throw away TALTZ if not used within the 5-day period at room temperature. See "Storing TALTZ" for more detail.
If you have more questions about how to use the TALTZ prefilled syringe:
- Call your child's healthcare provider
- Call Lilly at 1-800-545-5979 (1-800-Lilly-Rx)
- Visit www.taltz.com
Storing TALTZ
- Protect TALTZ from light.
- Store TALTZ in the refrigerator between 36°F to 46°F (2°C to 8°C).
  - If needed, you may store TALTZ at room temperature up to 86°F (30°C) for up to 5 days in the original carton to protect from light. Once TALTZ has been stored at room temperature, do not return to the refrigerator. Throw away TALTZ if it is not used within 5 days at room temperature.
  - Record the date when TALTZ is first removed from the refrigerator in the spaces provided on the carton.
- Do not freeze TALTZ. Do not use if TALTZ has been frozen.
- Do not shake TALTZ.
Keep TALTZ and all medicines out of the reach of children.
Read the Medication Guide for TALTZ inside this box to learn more about the medicine.
Eli Lilly and Company
Indianapolis, IN 46285, USA
US License Number 1891
TALTZ is a trademark of Eli Lilly and Company.
Copyright © 2024 Eli Lilly and Company. All rights reserved.
This Instructions for Use has been approved by the U.S. Food and Drug Administration.
Approved: February 2024
TAL-0.5ML-PFS-0001-IFU-20240202

TALTZ 20 mg Prefilled Syringe

INSTRUCTIONS FOR USE

TALTZ® [tol-t-s]
(ixekizumab)
injection, for subcutaneous use
20 mg/0.25 mL single-dose prefilled syringe

This Instructions for Use contains information on how to inject TALTZ.

Important Information You Need to Know Before Giving TALTZ Injection to Your Child

- Your child's healthcare provider or nurse should show you how to prepare and inject TALTZ using the prefilled syringe. Do not give the TALTZ prefilled syringe to your child until you have been shown how to inject TALTZ.
- Children ages 6 to 17 years of age should not inject themselves with TALTZ. You or an adult caregiver should prepare and give TALTZ injections to your child.
- You should read this Instructions for Use before injecting TALTZ and each time your child gets a refill. Keep the Instructions for Use and refer to them as needed.
- Each TALTZ prefilled syringe contains 1 dose (20 mg) of TALTZ. The syringe is for one-time use only. Do not share or reuse the TALTZ prefilled syringe. Your child may give or get an infection.
- Your child's healthcare provider may help you decide where on the body to inject the dose. Do not give an injection in an area of the skin that is tender, bruised, red or hard, or in an area of skin that is affected by psoriasis. Read the “Choose the injection site” section of these instructions to help you choose which area can work best.

- If you have vision problems, do not use TALTZ prefilled syringe without help.

Before you use the TALTZ prefilled syringe, read and carefully follow all the step-by-step instructions.
Parts of the TALTZ prefilled syringe
Step 1 | Preparing to Inject TALTZ
Step 1a | - Take the TALTZ prefilled syringe from the refrigerator. - Remove the prefilled syringe from the package. - Leave the needle cap on the syringe until you are ready to inject. - Wait 30 minutes to let the prefilled syringe warm to room temperature before you use it. - Do not microwave the syringe, run hot water over it, or leave it in direct sunlight. - Do not shake the prefilled syringe.
Step 1b | Gather the supplies needed for injection:; - 1 alcohol wipe - 1 cotton ball or piece of gauze - 1 sharps disposal container. See “Disposing of TALTZ”
Step 1c |  | Inspect the syringe. Leave the needle cap on the syringe until you are ready to inject.; - Make sure the name TALTZ appears on the label. - The medicine inside should be clear. Its color may be colorless to slightly yellow.; Do not use the prefilled syringe, and dispose of as directed by your child's healthcare provider or pharmacist if:; - the expiration date printed on the label has passed (see Figure A). - it looks damaged. - the medicine is frozen. - the medicine is cloudy, discolored, or has small particles. The medicine should look clear and colorless to slightly yellow.
Step 1d | Wash your hands with soap and water before you inject TALTZ.
Step 1e |  | Choose the injection site.; You may inject in the stomach area (abdomen) or in the thigh, or in the back of the arm (see Figure B). Do not give an injection into areas where the skin is tender, bruised, red or hard, or in an area of skin that is affected by psoriasis. Do not inject within 1 inch of the navel (belly button). Change (alternate) injection sites.; - Do not inject in the exact same spot every time. For example, if the last injection was in the left thigh, the next injection should be in the right thigh, the abdomen, or the back of either arm. - Talk with your child's healthcare provider about where on the body to best inject TALTZ.
Step 1f | Prepare the skin. Clean the injection site with an alcohol wipe. Let the injection site dry before you inject TALTZ.
Step 2 | Injecting TALTZ
Step 2a |  | Pull the needle cap off and throw it away (see Figure C).; - Do not put the needle cap back on. You could damage the needle or stick yourself by accident. - Do not touch the needle.
Step 2b |  | Gently pinch and hold a fold of skin where you will inject (see Figure D).
Step 2c |  | Insert the needle at a 45-degree angle to inject under the skin (subcutaneous injection) (see Figure E). Then gently let go of the skin. Make sure to keep the needle in place.; Let go of the skin before you push the plunger in (see Figure F).
Step 2d |  | Push in the plunger.; - Slowly push on the thumb pad to push the plunger all the way in until all the medicine is injected (see Figure G). - The gray syringe plunger should be pushed all the way to the needle end of the syringe. - You should see the gray syringe plunger at the bottom of the syringe body when the injection is complete (see Figure H). - Gently remove the needle from the skin. - Press a cotton ball or gauze over the injection site. Do not rub the injection site, as this may cause bruising. There may be slight bleeding. This is normal.; Do not put the needle cap back on the prefilled syringe.
Step 3 | Disposing of TALTZ
Step 3a
- Put the used TALTZ prefilled syringe in an FDA-cleared sharps disposal container right away after use (see Figure I). Do not throw away (dispose of) the TALTZ prefilled syringe in your household trash.
- If you do not have an FDA-cleared sharps disposal container, you may use a household container that is:
  - made of a heavy-duty plastic,
  - can be closed with a tight-fitting, puncture-resistant lid, without sharps being able to come out,
  - upright and stable during use,
  - leak-resistant, and
  - properly labeled to warn of hazardous waste inside the container.
- When your sharps disposal container is almost full, you will need to follow your community guidelines for the right way to dispose of your sharps disposal container. There may be state or local laws about how you should throw away needles and syringes. For more information about safe sharps disposal, and for specific information about sharps disposal in the state you live in, go to the FDA's website at: http://www.fda.gov/safesharpsdisposal
- Do not recycle your used sharps disposal container.
Commonly asked questions and answers.
Q. | What if I see air bubbles in the TALTZ prefilled syringe?
A. | It is normal to have air bubbles in the prefilled syringe.
Q. | What if there is a drop of liquid on the tip of the needle when I remove the needle cap?
A. | It is okay to see a drop of liquid on the tip of the needle.
Q. | What if I cannot push in the plunger?
A. | If the plunger is stuck or damaged:
 | - Do not continue to use the syringe
 | - Remove the needle from the skin
 | - Dispose of the syringe and get a new one
Q. | How can I tell if the injection is complete?
A. | When the injection is complete:
 | - The gray syringe plunger should be pushed all the way to the needle end of the syringe.
Q. | What if the syringe is left at room temperature for longer than 30 minutes?
A. | If needed, the syringe may be left out of the refrigerator at room temperature up to 86°F (30°C) for up to 5 days if protected from light. Throw away TALTZ if not used within the 5-day period at room temperature. See "Storing TALTZ" for more detail.
If you have more questions about how to use the TALTZ prefilled syringe:
- Call your child's healthcare provider
- Call Lilly at 1-800-545-5979 (1-800-Lilly-Rx)
- Visit www.taltz.com
Storing TALTZ
- Protect TALTZ from light.
- Store TALTZ in the refrigerator between 36°F to 46°F (2°C to 8°C).
  - If needed, you may store TALTZ at room temperature up to 86°F (30°C) for up to 5 days in the original carton to protect from light. Once TALTZ has been stored at room temperature, do not return to the refrigerator. Throw away TALTZ if it is not used within 5 days at room temperature.
  - Record the date when TALTZ is first removed from the refrigerator in the spaces provided on the carton.
- Do not freeze TALTZ. Do not use if TALTZ has been frozen.
- Do not shake TALTZ.
Keep TALTZ and all medicines out of the reach of children.
Read the Medication Guide for TALTZ inside this box to learn more about the medicine.
Eli Lilly and Company
Indianapolis, IN 46285, USA
US License Number 1891
TALTZ is a trademark of Eli Lilly and Company.
Copyright © 2024 Eli Lilly and Company. All rights reserved.
This Instructions for Use has been approved by the U.S. Food and Drug Administration.
Approved: February 2024
TAL-0.25ML-PFS-0001-IFU-20240202

PACKAGE CARTON – Taltz Autoinjector 80 mg

taltz®

(ixekizumab)
injection

80 mg/mL

For Subcutaneous Use Only

1 Single-Dose prefilled autoinjector

Discard any unused product.

NDC 0002-1445-11

1 x 1 mL Single-Dose prefilled autoinjector

Rx Only

Dispense enclosed Medication Guide to each patient.

Lilly

PACKAGE CARTON – Taltz Prefilled Syringe 80 mg

taltz®

(ixekizumab)
injection

80 mg/mL

For Subcutaneous Use Only

1 Single-Dose prefilled syringe

Discard any unused product.

NDC 0002-7724-11

1 x 1 mL Single-Dose prefilled syringe

Rx Only

Dispense enclosed Medication Guide to each patient.

Lilly

PACKAGE CARTON – Taltz Prefilled Syringe 40 mg

taltz®

(ixekizumab)
injection

40 mg/0.5 mL

For Subcutaneous Use Only

1 Single-Dose prefilled syringe

Discard any unused product.

NDC 0002-8905-11

1 x 0.5 mL Single-Dose prefilled syringe

Rx Only

Dispense enclosed Medication Guide to each patient.

Lilly

PACKAGE CARTON – Taltz Prefilled Syringe 20 mg

taltz®

(ixekizumab)
injection

20 mg/0.25 mL

For Subcutaneous Use Only

1 Single-Dose prefilled syringe

Discard any unused product.

NDC 0002-8900-11

1 x 0.25 mL Single-Dose prefilled syringe

Rx Only

Dispense enclosed Medication Guide to each patient.

Lilly